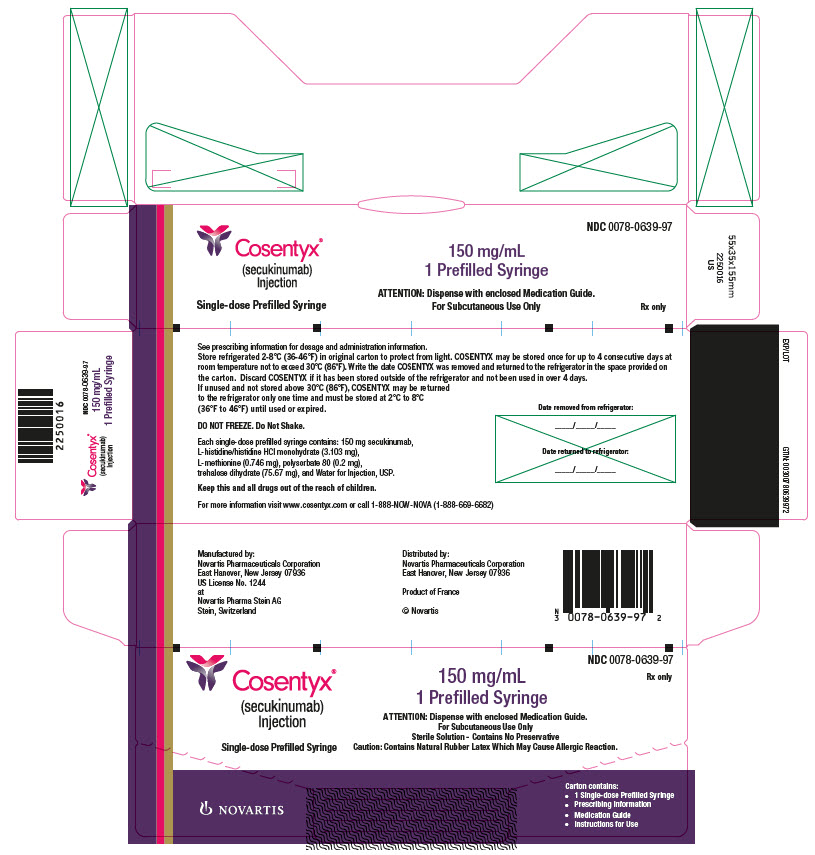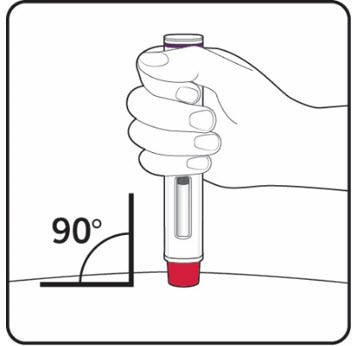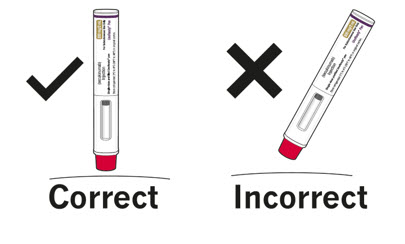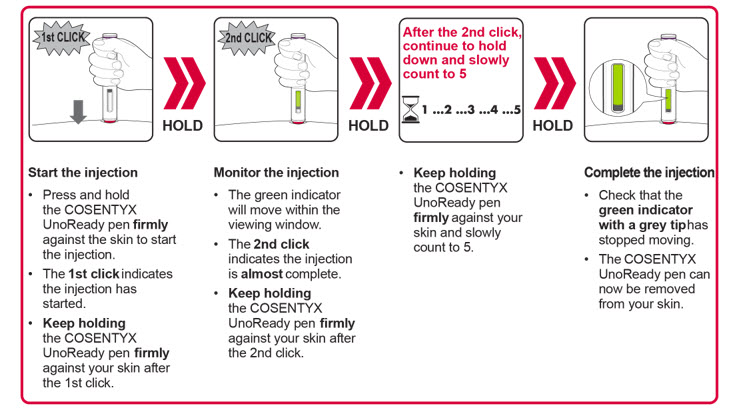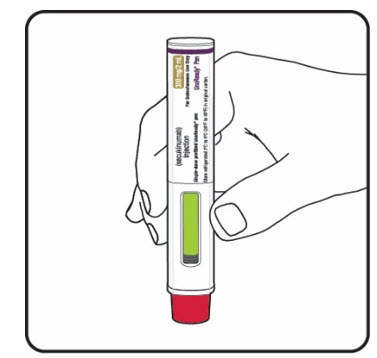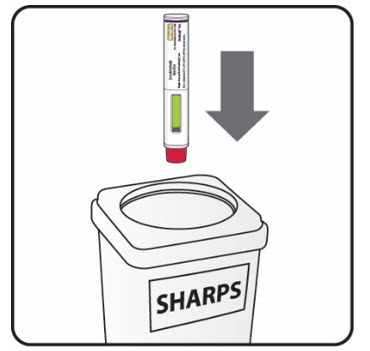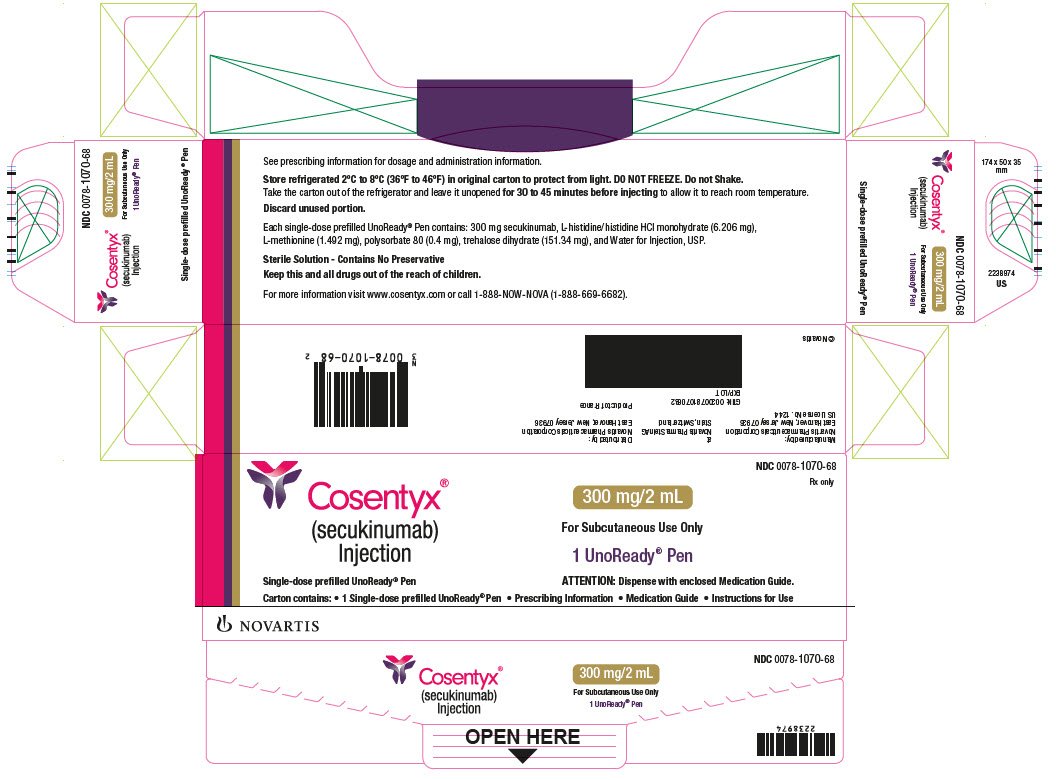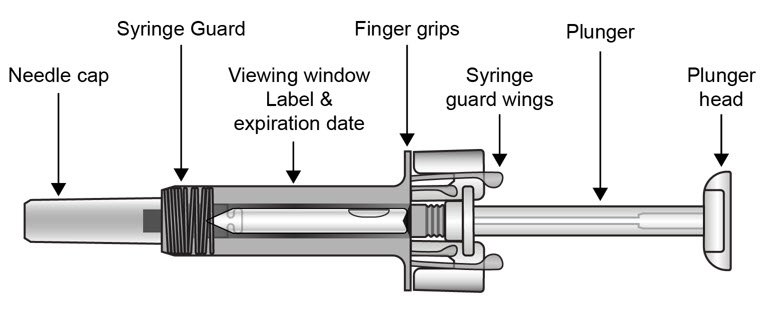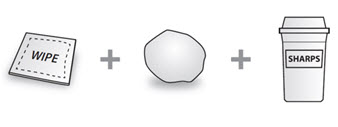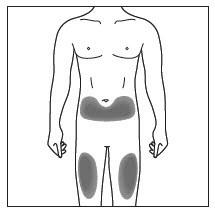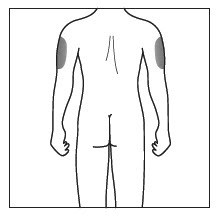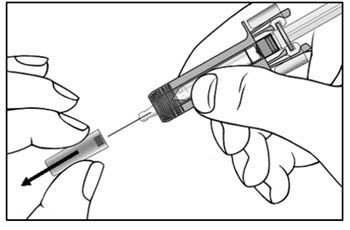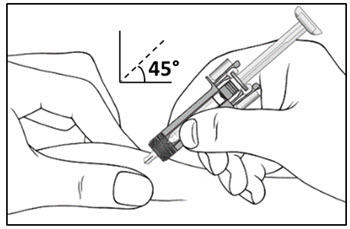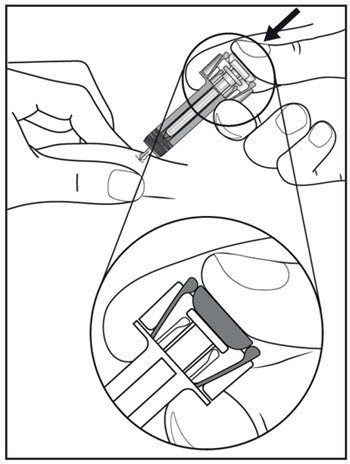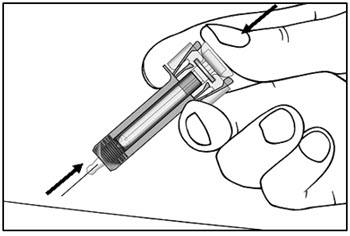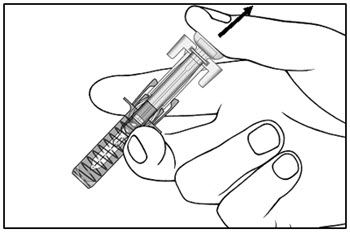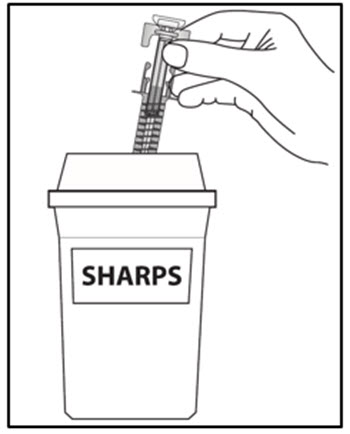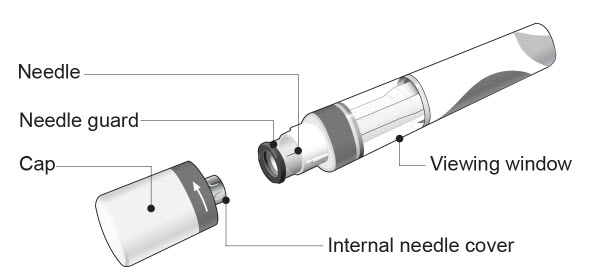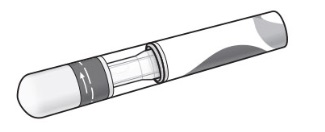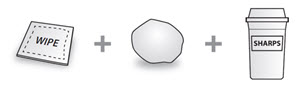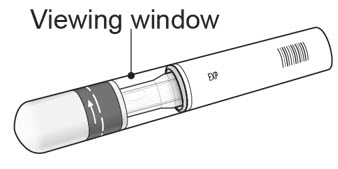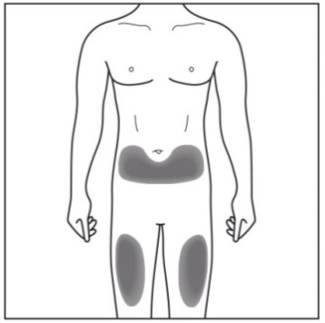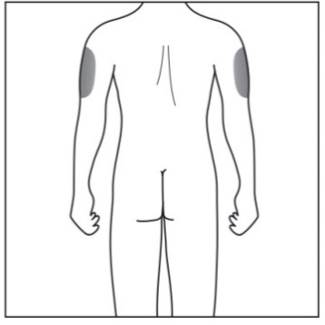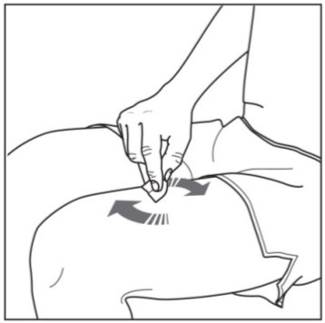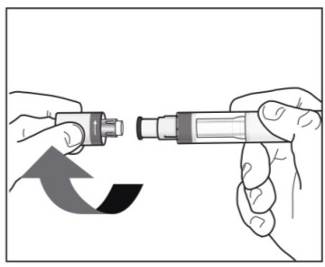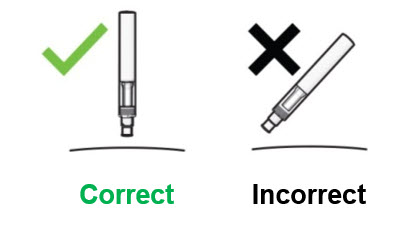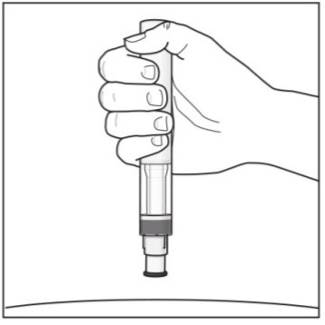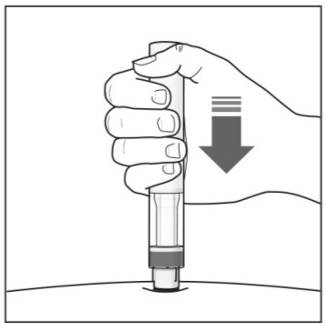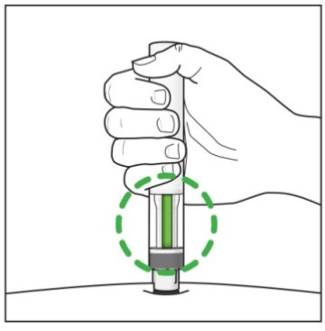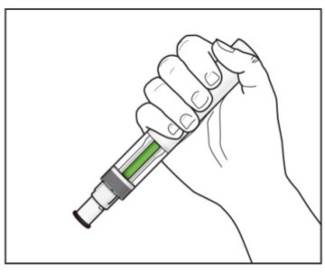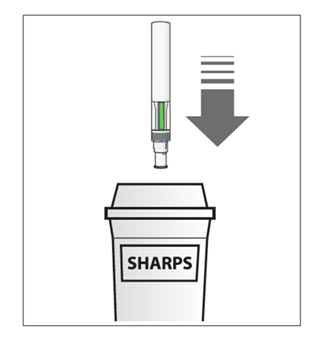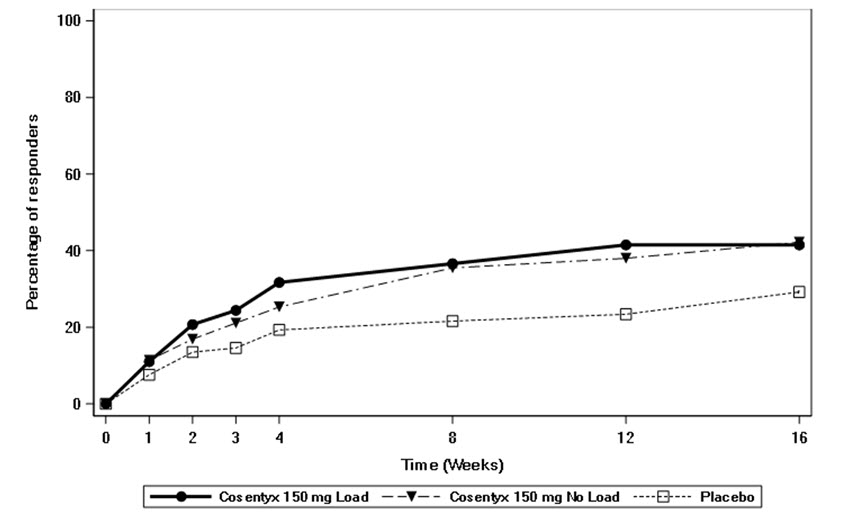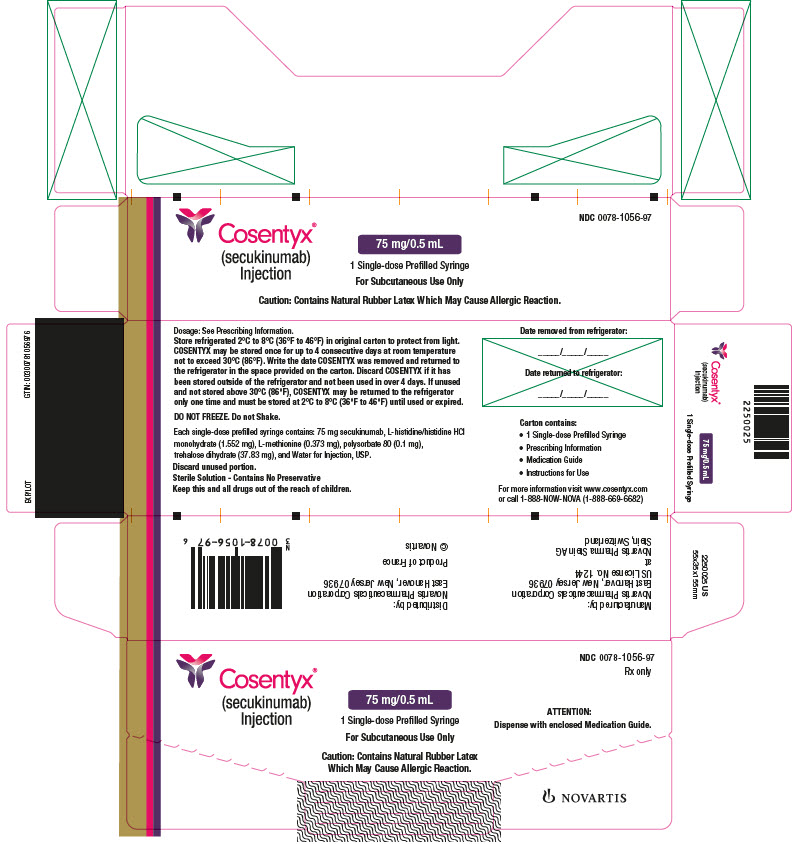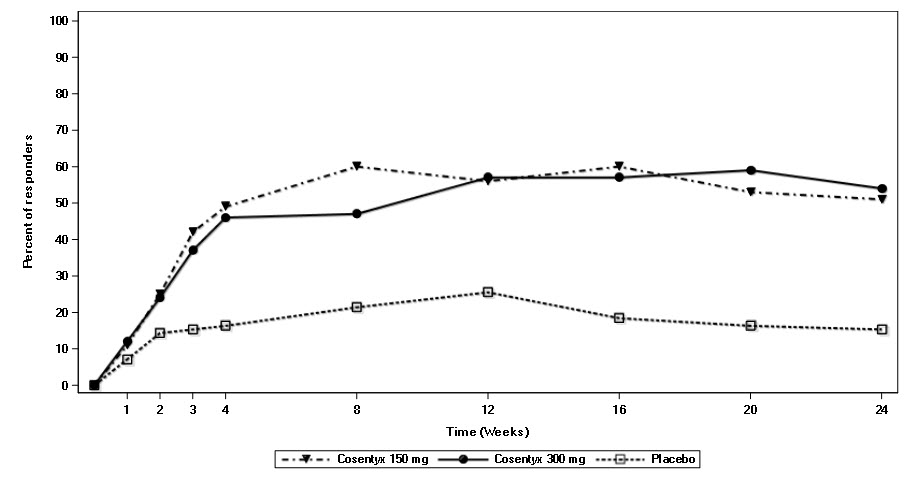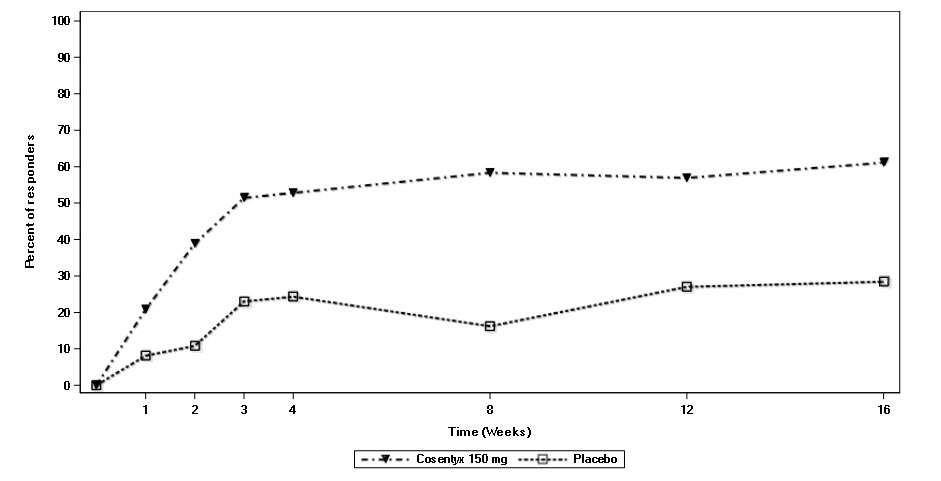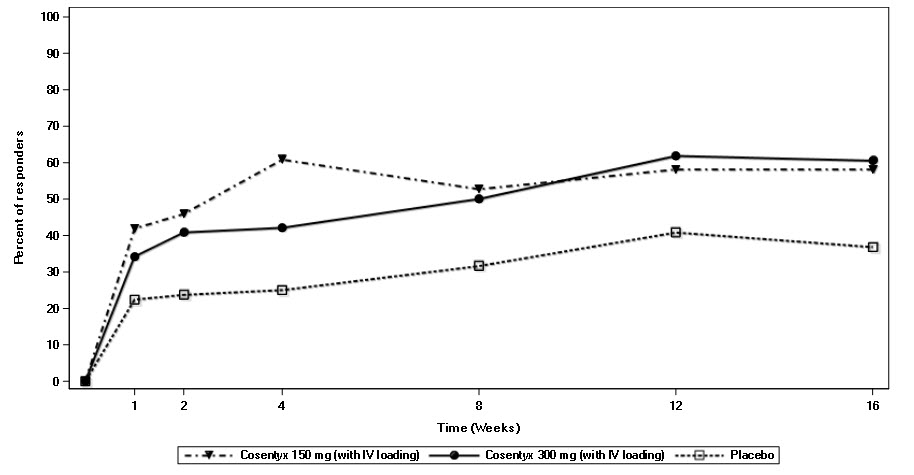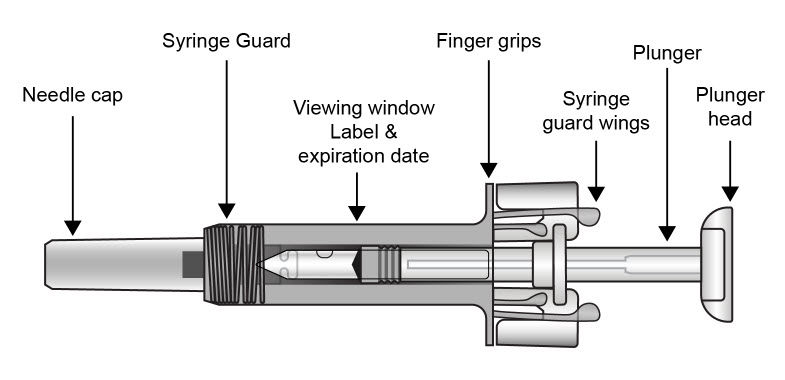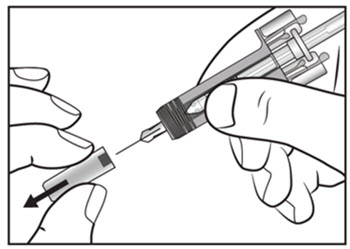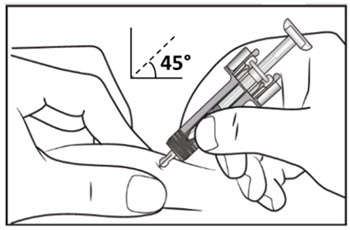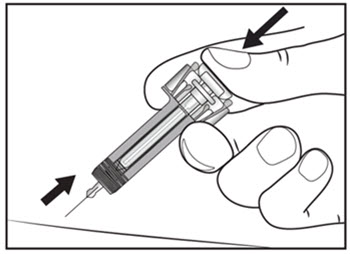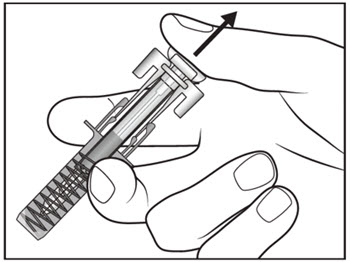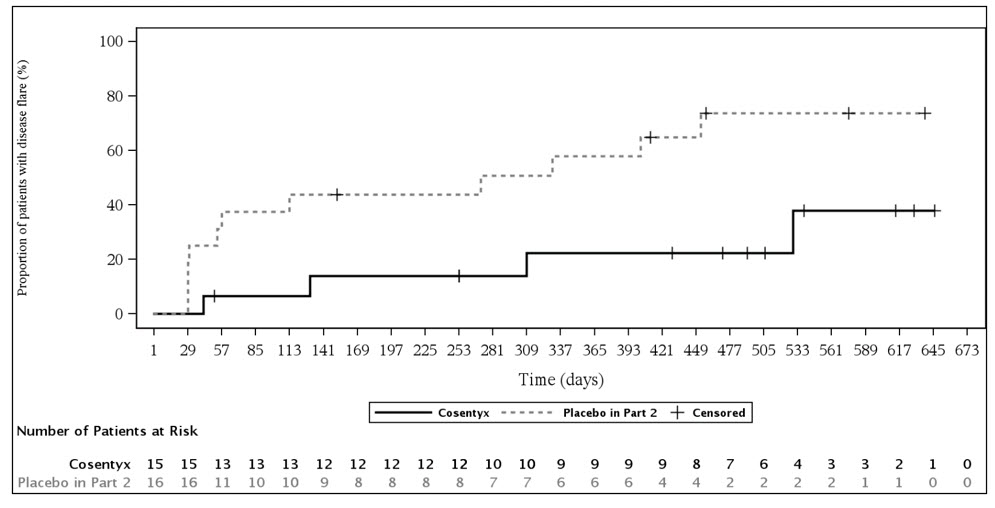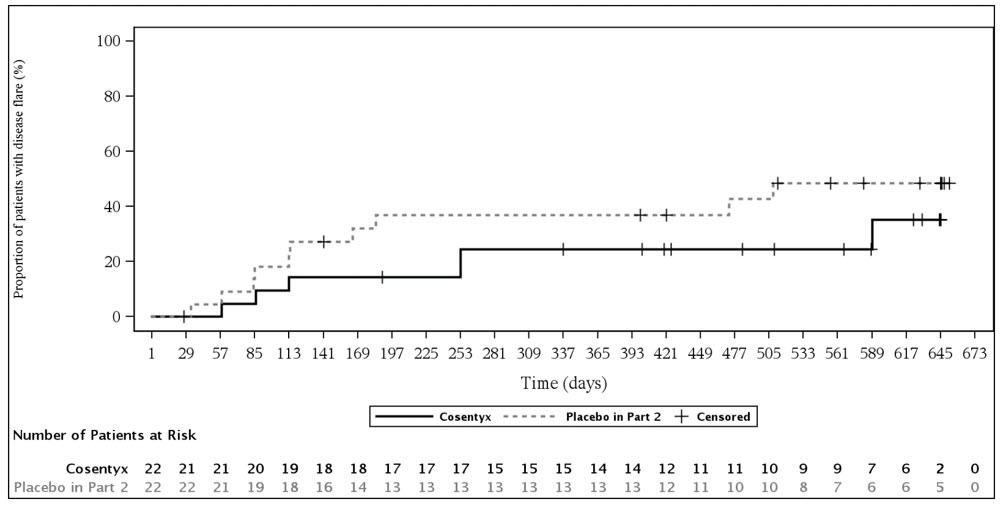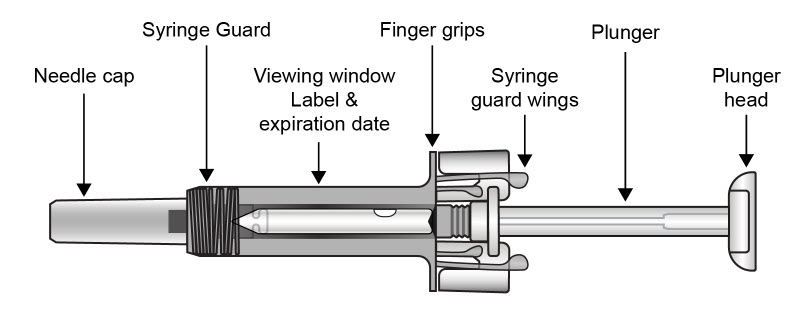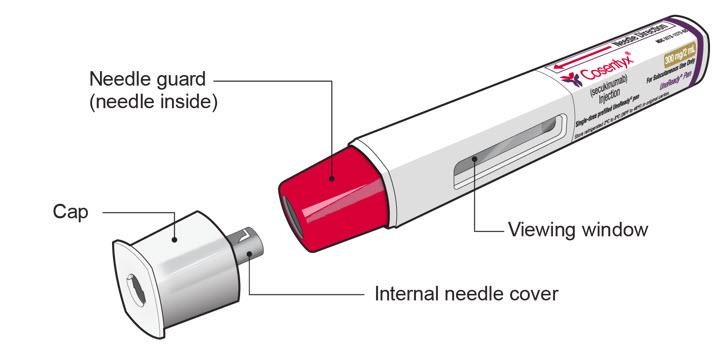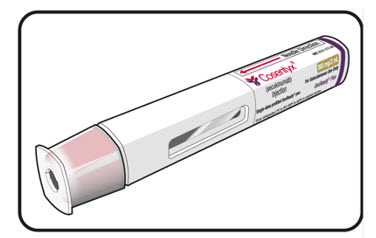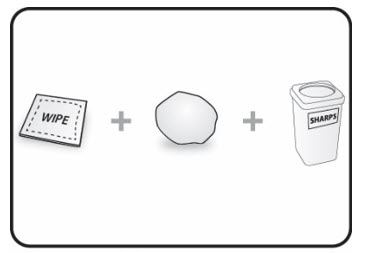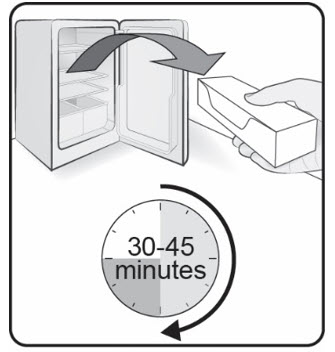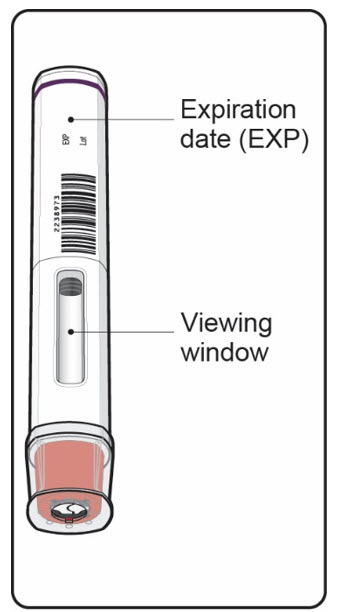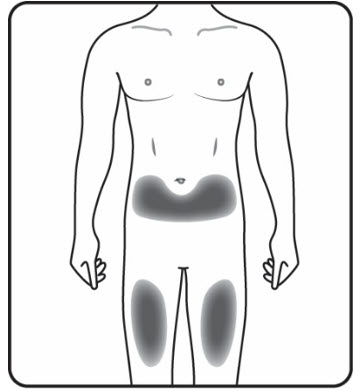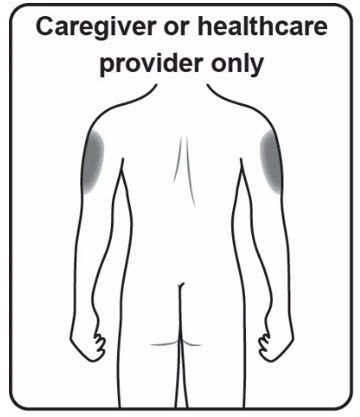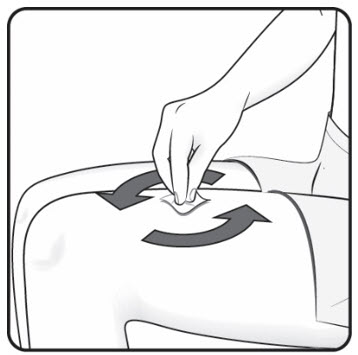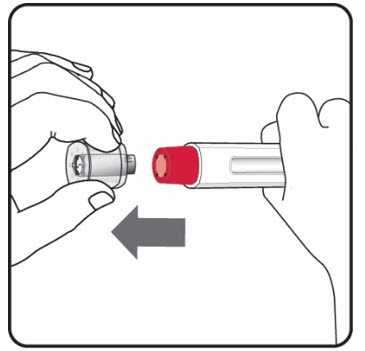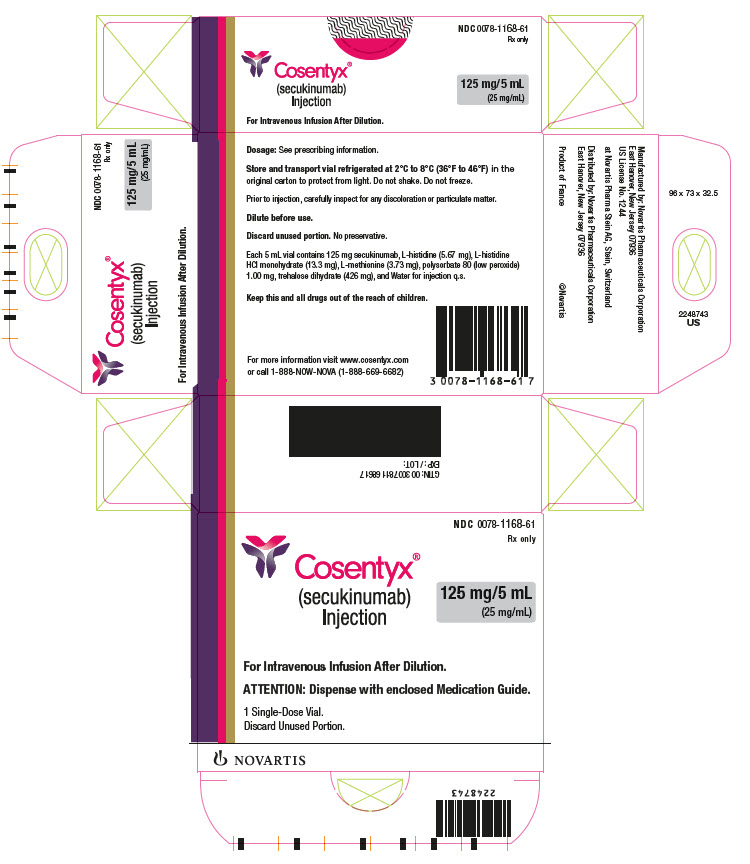 DRUG LABEL: COSENTYX
NDC: 0078-0639 | Form: INJECTION
Manufacturer: Novartis Pharmaceuticals Corporation
Category: prescription | Type: HUMAN PRESCRIPTION DRUG LABEL
Date: 20251212

ACTIVE INGREDIENTS: SECUKINUMAB 150 mg/1 mL
INACTIVE INGREDIENTS: HISTIDINE 3.103 mg/1 mL; HISTIDINE MONOHYDROCHLORIDE MONOHYDRATE 3.103 mg/1 mL; METHIONINE 0.746 mg/1 mL; POLYSORBATE 80 0.200 mg/1 mL; TREHALOSE DIHYDRATE 75.67 mg/1 mL; NITROGEN; WATER

HIGHLIGHTS OF PRESCRIBING INFORMATION

These highlights do not include all the information needed to use COSENTYX safely and effectively. See full prescribing information for COSENTYX.
COSENTYX® (secukinumab) injection, for subcutaneous or intravenous use
Initial U.S. Approval: 2015

RECENT MAJOR CHANGES

Contraindications (4) | 10/2024
Warnings and Precautions (5.2) | 10/2024

1 INDICATIONS AND USAGE

COSENTYX is a human interleukin-17A antagonist indicated for the treatment of:

- moderate to severe plaque psoriasis (PsO) in patients 6 years and older who are candidates for systemic therapy or phototherapy. (1.1)
- active psoriatic arthritis (PsA) in patients 2 years of age and older. (1.2)
- adults with active ankylosing spondylitis (AS). (1.3)
- adults with active non-radiographic axial spondyloarthritis (nr-axSpA) with objective signs of inflammation. (1.4)
- active enthesitis-related arthritis (ERA) in pediatric patients 4 years of age and older. (1.5)
- adults with moderate to severe hidradenitis suppurativa (HS). (1.6)

2 DOSAGE AND ADMINISTRATION

- Prior to COSENTYX initiation, complete all age-appropriate vaccinations, evaluate patients for tuberculosis (TB). (2.1). See Full Prescribing Information for instructions on preparation and administration of COSENTYX. (2.2, 2.10, 2.11)
- Administration of Intravenous Formulation: COSENTYX for intravenous use must be diluted prior to administration. Administer as an intravenous infusion after dilution over a period of 30 minutes. (2.11)
- Plaque Psoriasis:
  - Subcutaneous Dosage in Adults: Recommended dosage is 300 mg by subcutaneous injection at Weeks 0, 1, 2, 3, and 4 followed by 300 mg every 4 weeks. For some patients, a dose of 150 mg may be acceptable. (2.3)
  - Subcutaneous Dosage in Pediatric Patients 6 Years and Older: Recommended weight-based dosage is administered by subcutaneous injection at Weeks 0, 1, 2, 3, and 4 and every 4 weeks thereafter.
    - For patients < 50 kg (at the time of dosing), the dose is 75 mg.
    - For patients ≥ 50 kg (at the time of dosing), the dose is 150 mg. (2.3)

- Psoriatic Arthritis:
  Adult Patients
  Subcutaneous Dosage:
  - For PsA patients with coexistent moderate to severe PsO, use the dosage and administration for PsO. (2.3)
  - For other PsA patients, administer with or without a loading dosage.
    - With a loading dosage: 150 mg at Weeks 0, 1, 2, 3, and 4 and every 4 weeks thereafter
    - Without a loading dosage: 150 mg every 4 weeks
    - If a patient continues to have active PsA, consider a dosage of 300 mg every 4 weeks. (2.4)
  Intravenous Dosage:
  The recommended intravenous dosages are:
  - With a loading dosage: 6 mg/kg given at Week 0 as a loading dose, followed by 1.75 mg/kg every 4 weeks thereafter (max. maintenance dose 300 mg per infusion).
  - Without a loading dosage: 1.75 mg/kg every 4 weeks (max. maintenance dose 300 mg per infusion). (2.4)
  Pediatric Patients 2 Years and Older
  Subcutaneous Dosages: Administer by subcutaneous injection at Weeks 0, 1, 2, 3, and 4 and every 4 weeks thereafter:
  - For patients ≥ 15 kg and < 50 kg the dose is 75 mg.
  - For patients ≥ 50 kg the dose is 150 mg. (2.5)

- Ankylosing Spondylitis:
  Subcutaneous Dosage:
  Administer with or without a loading dosage.
  The recommended dosages are:
  - With a loading dosage: 150 mg at Weeks 0, 1, 2, 3, and 4 and every 4 weeks thereafter.
  - Without a loading dosage: 150 mg every 4 weeks.
  - If a patient continues to have active ankylosing spondylitis, consider a dosage of 300 mg every 4 weeks. (2.6)

Intravenous Dosage:

The recommended intravenous dosages are:

- With a loading dosage: 6 mg/kg given at Week 0 as a loading dose, followed by 1.75 mg/kg every 4 weeks thereafter (max. maintenance dose 300 mg per infusion).
- Without a loading dosage: 1.75 mg/kg every 4 weeks (max. maintenance dose 300 mg per infusion). (2.6)

- Non-Radiographic Axial Spondyloarthritis:
  Subcutaneous Dosage:
  Administer with or without a loading dosage. The recommended dosage is:
  - With a loading dosage: 150 mg at Weeks 0, 1, 2, 3, and 4 and every 4 weeks thereafter.
  - Without a loading dosage: 150 mg every 4 weeks. (2.7)

Intravenous Dosage:

The recommended intravenous dosages are:

- With a loading dosage: 6 mg/kg given at Week 0 as a loading dose, followed by 1.75 mg/kg every 4 weeks thereafter (max. maintenance dose 300 mg per infusion).
- Without a loading dosage: 1.75 mg/kg every 4 weeks (max. maintenance dose 300 mg per infusion). (2.7)

- Enthesitis-Related Arthritis: Recommended weight-based dosage is administered by subcutaneous injection at Weeks 0, 1, 2, 3, and 4 and every 4 weeks thereafter.
  - For patients ≥ 15 kg and < 50 kg the dose is 75 mg.
  - For patients ≥ 50 kg the dose is 150 mg. (2.8)

- Hidradenitis Suppurativa: Recommended dosage is 300 mg administered by subcutaneous injection at Weeks 0, 1, 2, 3 and 4 and every 4 weeks thereafter. If a patient does not adequately respond, consider increasing the dosage to 300 mg every 2 weeks. (2.9)

3 DOSAGE FORMS AND STRENGTHS

Subcutaneous Injection

- Injection: 300 mg/2 mL solution in a single-dose UnoReady® pen and in a single-dose prefilled syringe. (3)
- Injection: 150 mg/mL solution in a single-dose Sensoready® pen and in a single-dose prefilled syringe. (3)
- Injection: 75 mg/0.5 mL solution in a single-dose prefilled syringe (for pediatric patients). (3)

Intravenous Infusion

- Injection: 125 mg/5 mL solution in a single-dose vial. (3)

4 CONTRAINDICATIONS

Serious hypersensitivity to secukinumab or any excipients in COSENTYX. (4)

5 WARNINGS AND PRECAUTIONS

- Infections: Serious infections have occurred. Exercise caution when considering the use of COSENTYX in patients with a chronic infection or a history of recurrent infection. If a serious infection develops, discontinue COSENTYX until the infection resolves. (5.1)
- Hypersensitivity Reactions: If an anaphylactic reaction or other serious allergic reaction occurs, discontinue COSENTYX immediately and initiate appropriate therapy. (5.2)
- Tuberculosis (TB): Prior to initiating treatment with COSENTYX, evaluate for TB. (5.3)
- Inflammatory Bowel Disease (IBD): Cases of IBD were observed in clinical trials. Exercise caution when prescribing COSENTYX to patients with IBD. (5.4)
- Eczematous Eruptions: Cases of severe eczematous eruptions have occurred in patients receiving COSENTYX. (5.5)
- Immunizations: Avoid use of live vaccines in patients treated with COSENTYX. (5.7)

6 ADVERSE REACTIONS

Most common adverse reactions (> 1%) are nasopharyngitis, diarrhea, and upper respiratory tract infection. (6.1)

To report SUSPECTED ADVERSE REACTIONS, contact Novartis Pharmaceuticals Corporation at 1-888-669-6682 or FDA at 1-800-FDA-1088 or www.fda.gov/medwatch.

FULL PRESCRIBING INFORMATION

1 INDICATIONS AND USAGE

1.1 Plaque Psoriasis

COSENTYX® is indicated for the treatment of moderate to severe plaque psoriasis (PsO) in patients 6 years and older who are candidates for systemic therapy or phototherapy.

1.2 Psoriatic Arthritis

COSENTYX is indicated for the treatment of active psoriatic arthritis (PsA) in patients 2 years of age and older.

1.3 Ankylosing Spondylitis

COSENTYX is indicated for the treatment of adult patients with active ankylosing spondylitis (AS).

1.4 Non-Radiographic Axial Spondyloarthritis

COSENTYX is indicated for the treatment of adult patients with active non-radiographic axial spondyloarthritis (nr-axSpA) with objective signs of inflammation.

1.5 Enthesitis-Related Arthritis

COSENTYX is indicated for the treatment of active enthesitis-related arthritis (ERA) in pediatric patients 4 years of age and older.

1.6 Hidradenitis Suppurativa

COSENTYX is indicated for the treatment of adult patients with moderate to severe hidradenitis suppurativa (HS).

2 DOSAGE AND ADMINISTRATION

2.1 Testing and Procedures Prior to Treatment Initiation

Perform the following evaluations prior to COSENTYX initiation:

- Evaluate for active or latent tuberculosis (TB). COSENTYX initiation is not recommended in patients with active TB infection. Initiate treatment of latent TB prior to initiation of COSENTYX [see Warnings and Precautions (5.3)].
- Complete all age-appropriate vaccinations as recommended by current immunization guidelines prior to initiating treatment with COSENTYX [see Warnings and Precautions (5.7)].

2.2 Important Administration Instructions

- COSENTYX is for use under the guidance and supervision of a healthcare provider.
- UnoReady pens, Sensoready pens, and prefilled syringes are for subcutaneous use only.
- Solution in vials is for intravenous use in adult patients only.

Important Subcutaneous Administration Instructions

Adult patients may self-administer COSENTYX or be injected by a caregiver after proper training in subcutaneous injection technique.

Pediatric patients should not self-administer COSENTYX. An adult caregiver should prepare and inject COSENTYX after proper training in subcutaneous injection technique.

Administer each subcutaneous injection at a different anatomic location (such as upper arms, thighs, or any quadrant of abdomen) than the previous injection, and not into areas where the skin is tender, bruised, erythematous, indurated, or affected by psoriasis. Administration of subcutaneous COSENTYX in the upper, outer arm may be performed by a caregiver or healthcare provider.

The COSENTYX “Instructions for Use” for each presentation and strength contains more detailed instructions on the preparation and administration of COSENTYX for patients and caregivers [see Instructions for Use].

Important Intravenous Infusion Instructions

Intravenous infusion is only for use by a healthcare professional in a healthcare setting. Prepare COSENTYX intravenous infusion by diluting COSENTYX injection in vial(s) and administering based on patient body weight [see Dosage and Administration (2.11)]. Intravenous infusion may be administered only in adults with PsA, AS, and nr-axSPA.

2.3 Recommended Dosage in Plaque Psoriasis

Recommended Subcutaneous Dosage in Adults with PsO

The recommended dosage in adults with PsO is 300 mg by subcutaneous injection at Weeks 0, 1, 2, 3, and 4 and every 4 weeks thereafter. Each 300 mg dosage is given as one subcutaneous injection of 300 mg or as two subcutaneous injections of 150 mg.

For some patients, a dosage of 150 mg by subcutaneous injection at Weeks 0, 1, 2, 3, and 4 and every 4 weeks thereafter may be acceptable.

Recommended Subcutaneous Dosage in Pediatric Patients 6 Years of Age and Older with PsO

The recommended weight-based dosage in pediatric patients 6 years of age and older with PsO is administered by subcutaneous injection at Weeks 0, 1, 2, 3, and 4 and every 4 weeks thereafter.

- For patients < 50 kg (at the time of dosing), the recommended dose is 75 mg.
- For patients ≥ 50 kg (at the time of dosing), the recommended dose is 150 mg.

2.4 Recommended Dosage in Adults with Psoriatic Arthritis

COSENTYX may be administered with or without methotrexate.

Recommended Subcutaneous Dosage

For adult patients with PsA and with coexistent moderate to severe PsO, use the dosage and administration recommendations for adults with PsO [see Dosage and Administration (2.3)].

For other adult patients with PsA, administer COSENTYX with or without a loading dosage by subcutaneous injection.

The recommended dosage in adults with PsA:

- With a loading dosage is 150 mg at Weeks 0, 1, 2, 3, and 4 and every 4 weeks thereafter.
- Without a loading dosage is 150 mg every 4 weeks.
- If a patient continues to have active PsA, consider increasing the dosage to 300 mg by subcutaneous injection every 4 weeks. Each 300 mg dosage is given as one subcutaneous injection of 300 mg or as two subcutaneous injections of 150 mg.

Recommended Intravenous Dosage

COSENTYX injection for intravenous use (solution in vials) requires dilution prior to intravenous administration. The recommended intravenous dosage regimen in adults with PsA:

- With a loading dosage is 6 mg/kg loading dose given at Week 0, followed by 1.75 mg/kg every 4 weeks thereafter (maintenance dosage).
- Without a loading dosage is 1.75 mg/kg every 4 weeks.

Administer as an intravenous infusion over a period of 30 minutes [see Dosage and Administration (2.11)].

Total doses exceeding 300 mg per infusion are not recommended for the 1.75 mg/kg maintenance dose in adults with PsA [see Dosage and Administration (2.11)].

2.5 Recommended Dosage in Pediatric Patients 2 Years of Age and Older with Juvenile Psoriatic Arthritis

COSENTYX may be administered with or without methotrexate.

The recommended weight-based subcutaneous dosage in pediatric patients 2 years of age and older with PsA at Weeks 0, 1, 2, 3, and 4 and every 4 weeks thereafter is as follows:

- For patients ≥ 15 kg and < 50 kg, the recommended dose is 75 mg.
- For patients ≥ 50 kg, the recommended dose is 150 mg.

2.6 Recommended Dosage in Adults with Ankylosing Spondylitis

Recommended Subcutaneous Dosage

Administer COSENTYX with or without a loading dosage by subcutaneous injection in adult patients with active AS. The recommended dosage:

- With a loading dosage is 150 mg at Weeks 0, 1, 2, 3, and 4 and every 4 weeks thereafter.
- Without a loading dosage is 150 mg every 4 weeks.
- If a patient continues to have active AS, consider increasing the dosage to 300 mg every 4 weeks by subcutaneous injection. Each 300 mg dosage is given as one subcutaneous injection of 300 mg or as two subcutaneous injections of 150 mg.

Recommended Intravenous Dosage

COSENTYX injection for intravenous use (solution in vials) requires dilution prior to intravenous administration. The recommended intravenous dosage regimen in adult patients with active AS:

- With a loading dosage is 6 mg/kg loading dose given at Week 0, followed by 1.75 mg/kg every 4 weeks thereafter (maintenance dosage).
- Without a loading dosage is 1.75 mg/kg every 4 weeks.

Administer as an intravenous infusion over a period of 30 minutes [see Dosage and Administration (2.11)].

Total doses exceeding 300 mg per infusion are not recommended for the 1.75 mg/kg maintenance dose in patients with AS [see Dosage and Administration (2.11)].

2.7 Recommended Dosage in Adults with Non-Radiographic Axial Spondyloarthritis

Recommended Subcutaneous Dosage

Administer COSENTYX with or without a loading dosage by subcutaneous injection in adult patients with active nr-axSpA.

The recommended dosage:

- With a loading dosage is 150 mg at Weeks 0, 1, 2, 3, and 4 and every 4 weeks thereafter.
- Without a loading dosage is 150 mg every 4 weeks.

Recommended Intravenous Dosage

COSENTYX injection for intravenous use (solution in vials) requires dilution prior to intravenous administration. The recommended intravenous dosage regimen in adult patients with active nr-axSpA:

- With a loading dosage is 6 mg/kg loading dose given at Week 0, followed by 1.75 mg/kg every 4 weeks thereafter (maintenance dosage).
- Without a loading dosage is 1.75 mg/kg every 4 weeks.

Administer as an intravenous infusion over a period of 30 minutes [see Dosage and Administration (2.11)].

Total doses exceeding 300 mg per infusion are not recommended for the 1.75 mg/kg maintenance dose in patients with nr-axSpA [see Dosage and Administration (2.11)].

2.8 Recommended Dosage in Enthesitis-Related Arthritis

COSENTYX may only be administered as a subcutaneous injection in pediatric patients aged 4 years and older with active ERA.

The recommended weight-based dosage in pediatric patients 4 years of age and older with ERA is administered by subcutaneous injection at Weeks 0, 1, 2, 3, and 4 and every 4 weeks thereafter:

- For patients ≥ 15 kg and < 50 kg, the recommended dose is 75 mg.
- For patients ≥ 50 kg, the recommended dose is 150 mg.

2.9 Recommended Dosage in Hidradenitis Suppurativa

The recommended dose in adult patients with moderate to severe HS is 300 mg by subcutaneous injection at Weeks 0, 1, 2, 3 and 4 and every 4 weeks thereafter.

If a patient does not adequately respond, consider increasing the dosage to 300 mg every 2 weeks. Each 300 mg dosage is given as one subcutaneous injection of 300 mg or as two subcutaneous injections of 150 mg.

2.10 Preparation for Use of COSENTYX UnoReady Pen, Sensoready Pen and Prefilled Syringes

COSENTYX UnoReady pens, Sensoready pens and prefilled syringes are for subcutaneous injection only.

Before subcutaneous injection, remove COSENTYX from the refrigerator and allow COSENTYX to reach room temperature (15 to 30 minutes for the Sensoready pen, the 150 mg/mL and 75 mg/0.5 mL prefilled syringes; 30 to 45 minutes for the UnoReady pen and the 300 mg/2 mL prefilled syringe) without removing the needle cap.

The removable cap of the COSENTYX 150 mg/mL Sensoready pen and the COSENTYX prefilled syringes (150 mg/mL, 75 mg/0.5 mL) contain natural rubber latex and should not be handled by latex-sensitive individuals [see Warnings and Precautions (5.6)].

Inspect COSENTYX visually for particulate matter and discoloration prior to administration. COSENTYX injection is a clear to slightly opalescent, colorless to slightly yellow solution. Do not use if the liquid contains visible particles, is discolored or cloudy. Discard any unused product.

2.11 Preparation and Administration of COSENTYX for Intravenous Use

COSENTYX (for intravenous use) must be diluted prior to infusion. Using aseptic technique, prepare COSENTYX (for intravenous use) as follows:

Step 1. Volume Calculation

- Calculate the total volume of COSENTYX for intravenous use solution (in mL) required based on the patient’s actual body weight as follows:
  - Loading dose (6 mg/kg) is 0.24 mL/kg
  - Maintenance dose (1.75 mg/kg) is 0.07 mL/kg
- Use the number of vials based on total volume needed (one vial contains 5 mL of COSENTYX solution).

Step 2. Dilution

- Parenteral drug product should be inspected visually for particulate matter and discoloration prior to administration, whenever solution and container permit. Do not use if particulates or discolorations are noted.
- Follow Table 1 for recommended infusion bag size based on patient's body weight.

Table 1: Recommended Infusion Bags for Dilution and Preparation of COSENTYX for Intravenous Use Based on Body Weight and Dose
Body weight at time of dosing | For the loading dose (6 mg/kg) recommended infusion bag | For maintenance dose (1.75 mg/kg) recommended infusion bag
Greater than 52 kg | 100 mL | 100 mL
Less than or equal to 52 kg | 100 mL | 50 mL*
*If a 50 mL infusion bag is unavailable, then use a 100 mL infusion bag and withdraw and discard 50 mL of saline using aseptic technique and continue to follow the preparation and administration steps.

- From the infusion bag, withdraw and discard a volume of 0.9% Sodium Chloride Injection, USP, equal to the calculated volume of the COSENTYX solution required for the patient’s dose [see Dosage and Administration (2.4, 2.6, 2.7)].
- From the vial(s), withdraw the calculated volume (mL) of COSENTYX solution and add slowly into the 0.9% Sodium Chloride Injection, USP infusion bag. To mix the solution, gently invert the bag to avoid foaming. Do not shake.
- Discard unused COSENTYX product in vials because it does not contain preservatives.

Allow the diluted COSENTYX solution for infusion to warm to room temperature prior to the start of the intravenous infusion. Administer the diluted COSENTYX solution for infusion as soon as possible. If not administered immediately, store the diluted solution either:

- At room temperature 20ºC to 25ºC (68ºF to 77ºF) for no more than 4.5 hours from the start of the preparation (piercing the first vial) to the completion of infusion.
- Under refrigeration at 2°C to 8°C (36°F to 46°F) for no more than 24 hours, from the start of the time of the preparation (piercing the first vial) to the completion of infusion. This time includes the refrigeration of the diluted solution and the time to allow the diluted solution to warm to room temperature. Protect the diluted solution from light during storage under refrigeration.

Step 3. Administration

- Use only an infusion set with an in-line, sterile, non-pyrogenic, low protein-binding filter (pore size 0.2 micrometer).
- Administer the infusion at a flow rate of about 3.3 mL/minute for a 100 mL bag or 1.7 mL/min for a 50 mL bag (total administration time: 30 minutes).
- When administration is complete, flush the line with 0.9% Sodium Chloride Injection, USP to guarantee that all the COSENTYX solution for infusion in the line has been administered.
- Do not infuse COSENTYX concomitantly in the same intravenous line with other drugs. No physical or biochemical compatibility studies have been conducted to evaluate the IV coadministration of COSENTYX with other drugs.

3 DOSAGE FORMS AND STRENGTHS

Injection for subcutaneous use:

- 300 mg/2 mL as a clear to opalescent, colorless to slightly yellowish solution in a single-dose UnoReady pen
- 300 mg/2 mL as a clear to opalescent, colorless to slightly yellowish solution in a single-dose prefilled syringe
- 150 mg/mL as a clear to opalescent, colorless to slightly yellowish solution in a single-dose Sensoready pen
- 150 mg/mL as a clear to opalescent, colorless to slightly yellowish solution in a single-dose prefilled syringe
- 75 mg/0.5 mL as a clear to opalescent, colorless to slightly yellowish solution in a single-dose prefilled syringe (for pediatric patients less than 50 kg)

Injection for intravenous use:

- 125 mg/5 mL as a clear to opalescent, colorless to slightly yellowish solution in a single-dose vial for dilution prior to intravenous infusion (for healthcare professional use only).

4 CONTRAINDICATIONS

COSENTYX is contraindicated in patients with a previous serious hypersensitivity reaction to secukinumab or to any of the excipients in COSENTYX. Cases of anaphylaxis and angioedema have been reported during treatment with COSENTYX [see Warnings and Precautions (5.2)].

5 WARNINGS AND PRECAUTIONS

5.1 Infections

COSENTYX may increase the risk of infections. In clinical trials, a higher rate of infections was observed in COSENTYX treated subjects compared to placebo-treated subjects. In placebo-controlled clinical trials in subjects with moderate to severe PsO, higher rates of common infections, such as nasopharyngitis (11.4% versus 8.6%), upper respiratory tract infection (2.5% versus 0.7%) and mucocutaneous infections with candida (1.2% versus 0.3%) were observed in subjects treated with COSENTYX compared to placebo-treated subjects. A similar increase in risk of infection in subjects treated with COSENTYX was seen in placebo-controlled trials in subjects with PsA, AS and nr-axSpA. The incidence of some types of infections, including fungal infections, appeared to be dose-dependent in clinical trials [see Adverse Reactions (6.1)].

In the postmarketing setting, serious bacterial, viral, and fungal opportunistic infections, and some fatal infections have been reported in patients receiving IL-17 inhibitors including COSENTYX. Cases of Hepatitis B virus reactivation have been reported [see Adverse Reactions (6.2)].

Exercise caution when considering the use of COSENTYX in patients with a chronic infection or a history of recurrent infection. Instruct patients to seek medical advice if signs or symptoms suggestive of an infection occur. If a patient develops a serious infection, monitor the patient closely and discontinue COSENTYX until the infection resolves.

If signs of Hepatitis B virus reactivation occur, consult a hepatitis specialist. COSENTYX is not recommended for use in patients with active viral hepatitis.

5.2 Hypersensitivity Reactions

Serious hypersensitivity reactions including anaphylaxis, angioedema, and urticaria have been reported in COSENTYX treated subjects in clinical trials and in the post-marketing setting [see Adverse Reactions (6.1, 6.2)]. If an anaphylactic or other serious allergic reaction occurs, immediately discontinue administration of COSENTYX and initiate appropriate therapy [see Contraindications (4)].

5.3 Pre-Treatment Evaluation for Tuberculosis

Evaluate patients for active or latent TB infection prior to initiating treatment with COSENTYX. Avoid administration of COSENTYX to patients with active TB infection. Initiate treatment of latent TB prior to administering COSENTYX. Consider anti-TB therapy prior to initiation of COSENTYX in patients with a past history of latent or active TB in whom an adequate course of treatment cannot be confirmed. Monitor patients closely for signs and symptoms of active TB during and after treatment.

In the postmarketing setting, cases were reported where patients with a history of latent tuberculosis (TB) who were treated with COSENTYX developed active TB.

5.4 Inflammatory Bowel Disease

Inflammatory Bowel Disease (IBD) exacerbations, in some cases serious and/or leading to discontinuation of COSENTYX, occurred in COSENTYX treated subjects during clinical trials in PsO, PsA, AS, nr-axSpA, and HS. In adult subjects with HS, the incidence of IBD was higher in subjects who received COSENTYX 300 mg every 2 weeks (Ulcerative Colitis [UC] 1 case, EAIR 0.2/100 subject-years; Crohn`s Disease [CD] 1 case, EAIR 0.2/100 subject-years) compared to subjects who received COSENTYX 300 mg every 4 weeks (IBD 1 case, EAIR 0.2/100 subject-years). In addition, new onset IBD cases occurred in subjects treated with COSENTYX in clinical trials. In an exploratory trial in 59 subjects with active Crohn’s disease [COSENTYX is not approved for the treatment of Crohn`s disease], there were trends toward greater disease activity and increased adverse reactions in subjects treated with COSENTYX as compared to placebo-treated subjects.

Exercise caution when prescribing COSENTYX to patients with IBD. Patients treated with COSENTYX should be monitored for signs and symptoms of IBD [see Adverse Reactions (6.1)].

5.5 Eczematous Eruptions

In postmarketing reports, cases of severe eczematous eruptions, including atopic dermatitis-like eruptions, dyshidrotic eczema, and erythroderma, were reported in patients receiving COSENTYX; some cases resulted in hospitalization. The onset of eczematous eruptions was variable, ranging from days to months after the first dose of COSENTYX.

Treatment may need to be discontinued to resolve the eczematous eruption. Some patients were successfully treated for eczematous eruptions while continuing COSENTYX.

5.6 Risk of Hypersensitivity in Latex-Sensitive Individuals

The removable caps of the COSENTYX 150 mg/mL Sensoready pen and the COSENTYX 1 mL and 0.5 mL prefilled syringes contain natural rubber latex, which may cause a hypersensitivity reaction in latex-sensitive individuals. The safe use of COSENTYX 150 mg/mL Sensoready pen or 1 mL and 0.5 mL prefilled syringes in latex-sensitive individuals has not been studied.

5.7 Immunizations

Prior to initiating therapy with COSENTYX, consider completion of all age-appropriate immunizations according to current immunization guidelines. COSENTYX may alter a patient's immune response to live vaccines. Avoid use of live vaccines in patients treated with COSENTYX [see Clinical Pharmacology (12.2)].

6 ADVERSE REACTIONS

The following adverse reactions are discussed in greater detail elsewhere in the labeling:

- Infections [see Warnings and Precautions (5.1)]
- Hypersensitivity Reactions [see Warnings and Precautions (5.2)]
- Inflammatory Bowel Disease [see Warnings and Precautions (5.4)]
- Eczematous Eruptions [see Warnings and Precautions (5.5)]

6.1 Clinical Trials Experience

Because clinical trials are conducted under widely varying conditions, adverse reaction rates observed in the clinical trials of a drug cannot be directly compared to rates in the clinical trials of another drug and may not reflect the rates observed in practice.

Adverse Reactions in Clinical Trials of Subcutaneous COSENTYX

Adverse Reactions from Clinical Trials in Adults with PsO

A total of 3,430 adult subjects with PsO were treated with COSENTYX in controlled and uncontrolled clinical trials. Of these, 1,641 subjects were treated with COSENTYX for at least 1 year.

Four placebo-controlled Phase 3 trials in PsO subjects (Trials PsO1, PsO2, PsO3, and PsO4) were pooled to evaluate the safety of COSENTYX in comparison to placebo up to 12 weeks after treatment initiation. In total, 2,077 subjects were evaluated (691 in the COSENTYX 300 mg group, 692 in the COSENTYX 150 mg group, and 694 in the placebo group). Subjects randomized to COSENTYX received 300 mg or 150 mg doses subcutaneously at Weeks 0, 1, 2, 3, and 4 followed by the same dose every 4 weeks [see Clinical Studies (14)].

Table 2 summarizes the adverse reactions that occurred at a rate of at least 1% and at a higher rate in the COSENTYX groups than the placebo group during the 12-week placebo-controlled period of these trials.

Table 2: Adverse Reactions Reported by Greater Than 1% of Adult Subjects With PsO (and at a Higher Rate in Subjects Treated with COSENTYX) Through Week 12 in Trials PsO1, PsO2, PsO3, and PsO4
 | COSENTYX
Adverse reactions | 300 mg (N = 691) n (%) | 150 mg (N = 692) n (%) | Placebo (N = 694) n (%)
Nasopharyngitis | 79 (11.4) | 85 (12.3) | 60 (8.6)
Diarrhea | 28 (4.1) | 18 (2.6) | 10 (1.4)
Upper respiratory tract infection | 17 (2.5) | 22 (3.2) | 5 (0.7)
Rhinitis | 10 (1.4) | 10 (1.4) | 5 (0.7)
Oral herpes | 9 (1.3) | 1 (0.1) | 2 (0.3)
Pharyngitis | 8 (1.2) | 7 (1.0) | 0 (0)
Urticaria | 4 (0.6) | 8 (1.2) | 1 (0.1)
Rhinorrhea | 8 (1.2) | 2 (0.3) | 1 (0.1)

Adverse reactions that occurred in subjects treated with COSENTYX at rates less than 1% in the placebo-controlled period of Trials PsO1, PsO2, PsO3, and PsO4 through Week 12 included: sinusitis, tinea pedis, conjunctivitis, tonsillitis, oral candidiasis, impetigo, otitis media, otitis externa, IBD, increased liver transaminases, and neutropenia.

Infections

In the placebo-controlled period of the clinical trials in PsO (a total of 1,382 subjects treated with COSENTYX and 694 subjects treated with placebo up to 12 weeks), infections were reported in 28.7% of subjects treated with COSENTYX compared with 18.9% of subjects treated with placebo.

Over the entire treatment period (a total of 3,430 PsO subjects treated with COSENTYX for up to 52 weeks for the majority of subjects), infections were reported in 47.5% of subjects treated with COSENTYX (0.9 per subject-year of follow-up) and serious infections were reported in 1.2% of subjects treated with COSENTYX (0.015 per subject-year of follow-up).

Phase 3 data showed an increasing trend for some types of infection with increasing serum secukinumab concentrations. Candida infections, herpes viral infections, staphylococcal skin infections, and infections requiring treatment increased as serum secukinumab concentration increased.

In the PsO open-label extension of Trials PsO1 and PsO2 (median follow-up of 3.9 years), representing 3,582 subject-years of exposure, 74% of COSENTYX treated subjects reported infections (55 per 100 subject-years) and serious infections were reported in 4.5% of COSENTYX treated subjects (1.4 per 100 subject-years). Sepsis was reported in 5 COSENTYX treated subjects (0.2 per 100 subject-years).

Neutropenia was observed in controlled portion of clinical trials. Most cases of COSENTYX associated neutropenia were transient and reversible. No serious infections were associated with cases of neutropenia.

In the open-label extension of Trials PsO1 and PsO2, neutropenia (ANC < 1 x 10^9/L) was reported in 1% of COSENTYX treated subjects (0.3 per 100 subject-years). Some cases of serious infections were associated with neutropenia; however, the causal relationship was not established.

Inflammatory Bowel Disease

Cases of IBD, in some cases serious, were observed in subjects treated with COSENTYX in clinical trials. In the PsO program, with 3,430 subjects exposed to COSENTYX over the entire treatment period for up to 52 weeks (2,725 subject-years), there were 3 cases (0.11 per 100 subject-years) of exacerbation of CD, 2 cases (0.08 per 100 subject-years) of exacerbation of UC, and 2 cases (0.08 per 100 subject-years) of new onset UC. There were no IBD cases in placebo-treated subjects (N = 793; 176 subject-years) during the 12-week placebo-controlled period.

One case of exacerbation of Crohn’s disease in a subject treated with COSENTYX subject was reported in open-label portions of clinical trials in PsO.

Adverse Reactions from Clinical Trials in Pediatric Subjects with PsO

The safety of COSENTYX was assessed in two Phase 3 trials in pediatric subjects with PsO.

- The first was a randomized, double-blind, placebo and active-controlled, 236-week trial (Trial PsO8) that enrolled 162 pediatric subjects 6 years of age and older, with severe PsO (defined by PASI score ≥ 20, an IGA modified 2011 score of 4, and involving ≥ 10% of the body surface area [BSA]) who were candidates for systemic therapy. The 162 subjects were randomized to receive placebo, a biologic active control, or COSENTYX. In the COSENTYX groups, subjects with body weight (BW) less than 25 kg received 75 mg, subjects with BW 25 to less than 50 kg received either 75 mg or 150 mg (2 times the recommended dose), and subjects with BW of at least 50 kg received either 150 mg or 300 mg (2 times the recommended dose). Subjects were dosed at Weeks 0, 1, 2, 3, and 4 and every 4 weeks thereafter.
- The second trial was a randomized, open-label, 208-week trial (Trial PsO9; NCT03668613) of 84 pediatric subjects 6 years of age and older with moderate to severe PsO (defined by a PASI score ≥ 12, IGA mod 2011 score of ≥ 3, and BSA involvement of ≥ 10% at randomization) who were randomized into two COSENTYX arms [Arm 1: 75 mg for BW < 50 kg or 150 mg for ≥ 50 kg; and Arm 2: 75 mg for BW < 25 kg, 150 mg for BW ≥ 25 kg and < 50 kg, or 300 mg for BW ≥ 50 kg]. Subjects were dosed at Weeks 0, 1, 2, 3, and 4 and every 4 weeks thereafter.

The safety profile of COSENTYX reported in these trials was consistent with the safety profile reported in adult PsO trials.

Infections

One case of methicillin-resistant Staphylococcus aureus (MRSA) toxic shock syndrome (TSS) was reported in a COSENTYX treated pediatric subject during the placebo-controlled period.

In the pediatric safety pool, which includes all subjects who took at least one dose of COSENTYX during the treatment periods [198 subjects (287 subject-years)], 22 (11%) subjects reported ≥ Common Terminology Criteria for Adverse Events (CTCAE) Grade 2 neutropenia (≥ 1,000 to < 1,500 cells/mm^3) with 57% of subjects followed for one year or more and 30% of subjects followed for two years or more. During the placebo-controlled period, which included a total of 80 pediatric subjects treated with COSENTYX and 41 subjects treated with placebo up to 12 weeks, ≥ CTCAE Grade 2 neutropenia was reported in 3 (4%) of the subjects treated with COSENTYX compared with no subjects treated with placebo. No serious infections were associated with cases of neutropenia.

Adverse Reactions from Clinical Trials in Adults with PsA

COSENTYX was studied in two placebo-controlled PsA trials with 1,003 adult patients (703 patients on COSENTYX and 300 patients on placebo). Of the 703 patients who received COSENTYX, 299 patients received a subcutaneous loading dose of COSENTYX (PsA1) and 404 patients received an intravenous loading dose of secukinumab (PsA2) followed by COSENTYX administered by subcutaneous injection every four weeks. During the 16-week placebo-controlled period of the trials in patients with PsA, the overall proportion of patients with adverse events was similar in the secukinumab and placebo-treatment groups (59% and 58%, respectively). The adverse events that occurred at a proportion of at least 2% and at a higher proportion in the COSENTYX groups than the placebo groups during the 16-week placebo-controlled period were nasopharyngitis, upper respiratory tract infection, headache, nausea, and hypercholesterolemia. The safety profile observed in adult patients with PsA treated with COSENTYX is consistent with the safety profile in the PsO trials in adults.

Similar to the clinical trials in patients with PsO, there was an increased proportion of patients with infections in the COSENTYX groups (29%) compared to placebo group (26%).

There were cases of CD and UC in the secukinumab group that included patients who experienced either exacerbations or the development of new disease. There were three cases of IBD, of which two patients received secukinumab and one received placebo.

Adverse Reactions from Clinical Trials in Adults with AS

COSENTYX was studied in two placebo-controlled AS trials with 590 adult patients (394 patients on COSENTYX and 196 patients on placebo). Of the 394 patients who received COSENTYX, 145 patients received a subcutaneous load of COSENTYX (study AS1), and 249 received an intravenous loading dose of secukinumab (study AS2) followed by COSENTYX administered by subcutaneous injection every four weeks. During the 16-week placebo-controlled period of the trials in patients with AS, the overall proportion of patients with adverse events was higher in the secukinumab groups than the placebo-treatment groups (66% and 59%, respectively). The adverse events that occurred at a proportion of at least 2% and at a higher proportion in the COSENTYX groups than the placebo groups during the 16-week placebo-controlled period were nasopharyngitis, nausea, and upper respiratory tract infection. The safety profile observed in patients with AS treated with COSENTYX is consistent with the safety profile in PsO clinical trials. In a third controlled trial of AS (study AS3), the safety profile of the 300 mg dose of COSENTYX was consistent with the safety profile of the 150 mg dose of COSENTYX.

Similar to clinical trials in patients with PsO, there was an increased proportion of patients with infections in the COSENTYX groups (31%) compared to the placebo group (18%).

In the original AS program, with 571 patients exposed to COSENTYX, there were 8 cases of IBD during the entire treatment period [5 cases of Crohn’s (0.7 per 100 patient-years) and 3 cases of UC (0.4 per 100 patient-years)]. During the placebo-controlled 16-week period, there were 2 Crohn’s disease exacerbations and 1 new onset UC case that was a serious adverse event in patients treated with COSENTYX compared to none of the patients treated with placebo. During the remainder of the trial when all patients received COSENTYX, 1 patient developed Crohn’s disease, 2 patients had Crohn’s exacerbations, 1 patient developed UC, and 1 patient had an UC exacerbation.

Adverse Reactions from Clinical Trials in Adults with nr-axSpA

COSENTYX was studied in one randomized, double-blind, placebo-controlled nr-axSpA trial with 555 adult patients (185 patients received a loading COSENTYX dose, 184 patients did not receive a loading COSENTYX dose, and 186 patients received placebo). The safety profile for patients with nr-axSpA treated with COSENTYX was overall similar to the safety profile seen in patients with AS and other previous experience with COSENTYX. Patients in nr-axSpA1 trial who received the loading dosing regimen compared to those without the loading regimen, had higher incidence of infections and infestations (92 per 100 patient-years versus 72 per 100 patient-years), including nasopharyngitis, upper respiratory tract infection and urinary tract infection, and gastrointestinal disorders (27 per 100 patient-years versus 22 per 100 patient-years), including gastritis, lower abdominal pain, colitis, diarrhea, and hematochezia.

Adverse Reactions from Clinical Trials in Pediatric Patients with Juvenile Psoriatic Arthritis (JPsA) and ERA

COSENTYX was studied in one double-blind, placebo-controlled, event-driven, randomized trial in 86 pediatric patients aged 2 to less than 18 years old with JPsA and ERA. The safety profile reported in this trial was consistent with the safety profile of secukinumab.

Adverse Reactions from Clinical Trials in Adults with HS

COSENTYX was studied in two 52-week, randomized, double-blind, placebo-controlled HS trials with 1,084 adult subjects (361 subjects received COSENTYX 300 mg every 2 weeks, 360 subjects received COSENTYX 300 mg every 4 weeks, and 363 subjects received placebo) with a total of 901 subject-years of COSENTYX exposure (the median duration of exposure for subjects treated with COSENTYX was 360 days). The safety profile of COSENTYX observed in these HS trials was consistent with the known safety profile of COSENTYX observed in the PsO trials.

Infections

During the 16-week placebo-controlled period, subjects who received COSENTYX 300 mg every 2 weeks had the highest incidence of fungal infections (5.3%), compared to subjects who received COSENTYX 300 mg every 4 weeks (4.2%) and subjects who received placebo (2.8%). With longer exposure, the rate of fungal infections remained higher for subjects who received COSENTYX 300 mg every 2 weeks (14.7/100 subject-years) compared to subjects who received COSENTYX 300 mg every 4 weeks (10.1/100 subject-years). The majority of the cases were reported as non-serious, non-severe, and resolved with anti-fungal treatment.

Inflammatory Bowel Disease

In the open-labeled portion of HS clinical trials, five (0.7%) IBD adverse reactions were reported, all of which were serious and led to withdrawal of trial drug, and occurred only in subjects treated with COSENTYX 300 mg every 2 weeks. There were no IBD cases in subjects treated with COSENTYX 300 mg every 4 weeks.

Adverse Reactions of Intravenous COSENTYX

The safety of intravenous COSENTYX is based on the pharmacokinetic exposure and extrapolation of the established safety of subcutaneous COSENTYX in PsA, AS and nr-axSpA patients [see Clinical Pharmacology (12.3)].

6.2 Postmarketing Experience

The following adverse reactions have been reported during post-approval use of COSENTYX. Because they are reported voluntarily from a population of uncertain size, it is not always possible to reliably estimate their frequency or establish a causal relationship to drug exposure.

Immune system disorders: anaphylaxis, angioedema, systemic vasculitis

Skin and subcutaneous tissue disorders: eczematous eruptions (atopic dermatitis-like eruptions, dyshidrotic eczema, and erythroderma), cutaneous vasculitis, pyoderma gangrenosum

Infections: bacterial, viral, and fungal opportunistic infections, including esophageal candidiasis, tracheobronchial candidiasis, cutaneous aspergillosis, cytomegalovirus gastroenteritis/colitis, herpes simplex encephalitis, herpes simplex keratitis, Pneumocystis jiroveci pneumonia, Hepatitis B virus reactivation, histoplasmosis, toxoplasmosis

7 DRUG INTERACTIONS

Certain CYP450 Substrates

Increased concentrations of cytokines (e.g., IL-17) during chronic inflammation associated with certain diseases including PsO, PsA, AS, nr-axSpA, ERA, and HS may suppress the formation of CYP enzymes.

Upon initiation or discontinuation of COSENTYX in patients who are receiving concomitant CYP450 substrates, particularly those where minimal decreases in the concentration may reduce CYP substrate effectiveness or minimal increases in the concentration may increase CYP substrate adverse reactions, consider monitoring for therapeutic effect or concentration of the CYP substrate and consider dosage adjustment of the CYP substrate as needed [see Clinical Pharmacology (12.3)].

8 USE IN SPECIFIC POPULATIONS

8.1 Pregnancy

Risk Summary

Limited available human data with COSENTYX use in pregnant women are insufficient to inform a drug-associated risk of adverse developmental outcomes. In an embryo-fetal development study, no adverse developmental effects were observed in infants born to pregnant monkeys after subcutaneous administration of secukinumab during organogenesis at doses up to 30 times the maximum recommended human dose (MRHD) (see Data).

The background risk of major birth defects and miscarriage for the indicated population is unknown; however, the background risk in the U.S. general population of major birth defects is 2% to 4% and of miscarriage is 15% to 20% of clinically recognized pregnancies.

Data

Animal Data

An embryo-fetal development study was performed in cynomolgus monkeys with secukinumab. No malformations or embryo-fetal toxicity were observed in fetuses from pregnant monkeys that were administered secukinumab weekly by the subcutaneous route during the period of organogenesis at doses up to 30 times the MRHD (on a mg/kg basis at a maternal dose of 150 mg/kg).

A pre- and post-natal development toxicity study was performed in mice with a murine analog of secukinumab. No treatment-related effects on functional, morphological, or immunological development were observed in fetuses from pregnant mice that were administered the murine analog of secukinumab on gestation days 6, 11, and 17 and on postpartum days 4, 10, and 16 at doses up to 150 mg/kg/dose.

8.2 Lactation

Risk Summary

It is not known whether secukinumab is excreted in human milk or absorbed systemically after ingestion. There are no data on the effects of COSENTYX on the breastfed child or the effects on milk production. The developmental and health benefits of breastfeeding should be considered along with the mother’s clinical need for COSENTYX and any potential adverse effects on the breastfed child from COSENTYX or from the underlying maternal condition.

8.4 Pediatric Use

Subcutaneous Administration

Pediatric Plaque Psoriasis

The safety and effectiveness of COSENTYX have been established for the treatment of moderate to severe PsO in pediatric patients aged 6 years and older who are candidates for systemic therapy or phototherapy [see Adverse Reactions (6.1) and Clinical Studies (14.2)].

Safety and effectiveness of COSENTYX in pediatric patients with PsO below the age of 6 years have not been established.

Juvenile Psoriatic Arthritis

The safety and effectiveness of COSENTYX have been established for the treatment of active JPsA in pediatric patients aged 2 years and older who weigh 15 kg or more [see Adverse Reactions (6.1) and Clinical Studies (14.6)].

The safety and effectiveness of COSENTYX in pediatric patients less than 2 years of age with JPsA or with a body weight less than 15 kg has not been established.

Enthesitis-Related Arthritis

The safety and effectiveness of COSENTYX for the treatment of active ERA in pediatric patients aged 4 years and older who weigh 15 kg or more has been established [see Adverse Reactions (6.1) and Clinical Studies (14.6)].

The safety and effectiveness of COSENTYX in pediatric patients below the age of 4 years old or with body weight less than 15 kg have not been established.

Hidradenitis Suppurativa

The safety and effectiveness of COSENTYX in pediatric patients with HS have not been established.

Intravenous Administration

The safety and effectiveness of intravenous COSENTYX in pediatric patients have not been established.

8.5 Geriatric Use

Of the 3,430 PsO subjects exposed to subcutaneous COSENTYX in clinical trials, a total of 230 (7%) were 65 years of age or older, and 32 (1%) subjects were 75 years of age or older. Although no differences in safety or efficacy were observed between subjects 65 years of age or older and younger adult subjects, the number of subjects 65 years of age and older was not sufficient to determine whether they respond differently from younger adult subjects.

Of the 1,060 subjects with HS exposed to COSENTYX in clinical trials, a total of 14 (1.3%) were 65 years of age and older. Clinical trials in HS did not include sufficient numbers of subjects 65 years of age and older to determine whether they respond differently from younger adult subjects.

10 OVERDOSAGE

In the event of overdosage, it is recommended that the patient be monitored for any signs or symptoms of adverse reactions and appropriate symptomatic treatment be instituted. Consider contacting the Poison Help line (1-800-222-1222) or a medical toxicologist for additional overdose management recommendations.

11 DESCRIPTION

Secukinumab, a recombinant human monoclonal IgG1/κ antibody, is an interleukin-17A antagonist. It is expressed in a recombinant Chinese Hamster Ovary (CHO) cell line. Secukinumab has a molecular mass of approximately 151 kDa; both heavy chains of secukinumab contain oligosaccharide chains.

COSENTYX Injection for Subcutaneous Use

COSENTYX injection is a sterile, preservative-free, clear to slightly opalescent, colorless to slightly yellow solution for subcutaneous use. COSENTYX injection is supplied in a single-dose 300 mg/2 mL UnoReady pen with a 27-gauge fixed ½-inch needle, a single-dose 150 mg/mL Sensoready pen with a 27-gauge fixed ½-inch needle, or a single-dose prefilled syringe (300 mg/2 mL, 150 mg/mL, 75 mg/0.5 mL) with a 27-gauge fixed ½-inch needle. The removable cap of the COSENTYX 150 mg/mL Sensoready pen or 1 mL and 0.5 mL prefilled syringes contains natural rubber latex.

Each COSENTYX 300 mg/2 mL UnoReady pen or 300 mg/2 mL prefilled syringe contains 300 mg of secukinumab formulated in: L-histidine/histidine hydrochloride monohydrate (6.206 mg), L-methionine (1.492 mg), polysorbate 80 (0.4 mg), trehalose dihydrate (151.34 mg), and Sterile Water for Injection, USP, at pH of 5.8.

Each COSENTYX 150 mg/mL Sensoready pen or 150 mg/mL prefilled syringe contains 150 mg of secukinumab formulated in: L-histidine/histidine hydrochloride monohydrate (3.103 mg), L-methionine (0.746 mg), polysorbate 80 (0.2 mg), trehalose dihydrate (75.67 mg), and Sterile Water for Injection, USP, at pH of 5.8.

Each COSENTYX 75 mg/0.5 mL prefilled syringe contains 75 mg of secukinumab formulated in: L-histidine/histidine hydrochloride monohydrate (1.552 mg), L-methionine (0.373 mg), polysorbate 80 (0.1 mg), trehalose dihydrate (37.83 mg), and Sterile Water for Injection, USP, at pH of 5.8.

COSENTYX Injection for Intravenous Use

COSENTYX solution is supplied as a sterile, preservative free, clear to opalescent, colorless to slightly yellowish solution in single-dose vials for intravenous infusion after dilution.

Each COSENTYX vial contains 125 mg of secukinumab formulated in: L-histidine (5.67 mg), L-histidine hydrochloride monohydrate (13.3 mg), L-methionine (3.73 mg), polysorbate 80 (1 mg), trehalose dihydrate (426 mg), and Sterile Water for Injection, USP, at pH of 5.8.

12 CLINICAL PHARMACOLOGY

12.1 Mechanism of Action

Secukinumab is a human IgG1 monoclonal antibody that selectively binds to the interleukin-17A (IL-17A) cytokine and inhibits its interaction with the IL-17 receptor. IL-17A is a naturally occurring cytokine that is involved in normal inflammatory and immune responses. Secukinumab inhibits the release of proinflammatory cytokines and chemokines.

12.2 Pharmacodynamics

Elevated levels of IL-17A are found in psoriatic plaques and in HS lesions. Treatment with COSENTYX may reduce epidermal neutrophils and IL-17A levels in psoriatic plaques. Serum levels of total IL-17A (free and secukinumab-bound IL-17A) measured at Week 4 and Week 12 were increased following secukinumab treatment. These pharmacodynamic activities are based on small exploratory trials. The relationship between these pharmacodynamic activities and the mechanism(s) by which secukinumab exerts its clinical effects is unknown.

Increased numbers of IL-17A producing lymphocytes and innate immune cells and increased levels of IL-17A have been found in the blood of patients with PsA and AS. Increased numbers of IL-17A producing lymphocytes have also been found in patients with nr-axSpA.

Immune Response to Non-Live Vaccines During Treatment

Healthy individuals who received a single 150 mg dose of COSENTYX 2 weeks prior to vaccination with a non-U.S.-approved group C meningococcal polysaccharide conjugate vaccine and a non-U.S.-approved inactivated seasonal influenza vaccine had similar antibody responses compared to individuals who did not receive COSENTYX prior to vaccination. The clinical effectiveness of meningococcal and influenza vaccines has not been assessed in patients undergoing treatment with COSENTYX [see Warnings and Precautions (5.7)].

12.3 Pharmacokinetics

Pharmacokinetics Following Subcutaneous Administration

The observed pharmacokinetics (PK) of secukinumab administered subcutaneously in patients with PsO, PsA, AS and nr-axSpA were similar. The secukinumab PK is also similar in pediatric patients with ERA and PsO for the same weight tiered dosing regimen.

The mean steady-state trough concentration of secukinumab was approximately 26% lower in HS subjects than that of PsO subjects.

Absorption

Following a single subcutaneous dose of either 150 mg or 300 mg (administered as two injections of 150 mg) of COSENTYX in PsO subjects, secukinumab reached peak mean (± SD) serum concentrations (Cmax) of 13.7 ± 4.8 mcg/mL and 27.3 ± 9.5 mcg/mL, respectively, by approximately 6 days post dose.

Following multiple subcutaneous doses of COSENTYX (administered as one or two injections of 150 mg), the mean (± SD) serum trough concentrations of secukinumab ranged from 22.8 ± 10.2 mcg/mL (150 mg) to 45.4 ± 21.2 mcg/mL (300 mg) at Week 12. At the 300 mg dose at Week 4 and Week 12, the mean trough concentrations resulted from the Sensoready pen were approximately 30% higher than those from the prefilled syringe. Following multiple subcutaneous doses of 300 mg administered via the 300 mg/2 mL UnoReady pen, the mean serum trough concentrations of secukinumab were generally consistent with those in the previous Sensoready pen study used to deliver 300 mg.

Steady-state concentrations of secukinumab were achieved by Week 24 following the every 4-week COSENTYX dosing regimens. The mean (± SD) steady-state trough concentrations ranged from 16.7 ± 8.2 mcg/mL (150 mg) to 34.4 ± 16.6 mcg/mL (300 mg administered as two injections of 150 mg).

In healthy subjects and subjects with PsO, secukinumab bioavailability ranged from 55% to 77% following subcutaneous COSENTYX dose of 150 mg or 300 mg (administered as two injections of 150 mg).

Following subcutaneous administrations of 300 mg of COSENTYX at Weeks 0, 1, 2, 3, and 4 and then every 2 weeks thereafter, steady-state concentrations of secukinumab were achieved by Week 24 in both HS trials. The mean (± SD) steady-state trough concentrations were 55.7 ± 28.9 mcg/mL and 50.5 ± 28.2 mcg/mL in HS Trial 1 and HS Trial 2, respectively.

Distribution

The mean volume of distribution during the terminal phase (Vz) following a single intravenous administration ranged from 7.10 to 8.60 L in PsO subjects.

Secukinumab concentrations in interstitial fluid in lesional and non-lesional skin of PsO subjects ranged from 27% to 40% of those in serum at 1 and 2 weeks after a single subcutaneous dose of COSENTYX 300 mg (administered as two injections of 150 mg).

Elimination

Metabolism

The metabolic pathway of secukinumab has not been characterized. As a human IgG1κ monoclonal antibody secukinumab is expected to be degraded into small peptides and amino acids via catabolic pathways in the same manner as endogenous IgG.

Excretion

The mean systemic clearance (CL) ranged from 0.14 L/day to 0.22 L/day and the mean half-life ranged from 22 to 31 days in PsO subjects following intravenous and subcutaneous administration across all PsO trials.

In a population PK analysis, the mean systemic CL in subjects with HS was 0.26 L/day. The mean elimination half-life, as estimated from population PK analysis, was 23 days in HS subjects.

Dose Linearity

Secukinumab exhibited dose-proportional PK in subjects with PsO over a dose range from 25 mg (approximately 0.083 times the recommended dose) to 300 mg following subcutaneous administrations.

Weight

Secukinumab clearance and volume of distribution increase as body weight increases.

Specific Populations

Patients with Hepatic or Renal Impairment

No formal trial of the effect of hepatic or renal impairment on the PK of secukinumab was conducted.

Geriatric Patients

Population PK analysis indicated that the clearance of secukinumab was not significantly influenced by age in adult subjects with PsO, PsA and AS. Subjects who are 65 years or older had apparent clearance of secukinumab similar to subjects less than 65 years old.

Pediatric Patients

In a pool of the two pediatric trials, subjects with moderate to severe PsO (6 years of age and older) were administered subcutaneous COSENTYX at the recommended pediatric dosing regimen. At Week 24, secukinumab steady state mean ± SD serum trough concentrations were 32.6 ± 10.8 mcg/mL (n = 8), 19.8 ± 6.96 mcg/mL (n = 24), and 27.3 ± 10.1 mcg/mL (n = 36), in subjects who weighed less than 25 kg and received 75 mg of subcutaneous COSENTYX, subjects who weighed at least 25 kg and less than 50 kg and received 75 mg of subcutaneous COSENTYX, and subjects who weighed at least 50 kg and received 150 mg of subcutaneous COSENTYX, respectively.

In a pediatric trial, JPsA and ERA patients (2 to less than 18 years of age) were administered subcutaneous COSENTYX at the recommended pediatric dosing regimen. At Week 24, patients who weighed at least 15 kg and less than 50 kg, and patients who weighed at least 50 kg had a mean ± SD steady-state trough concentration of 25.2 ± 5.45 mcg/mL (n = 10) and 27.9 ± 9.57 mcg/mL (n = 19), respectively.

Drug Interactions

Cytochrome P450 Substrates

In adult subjects with PsO, midazolam (CYP3A4 substrate) PK was similar when administered alone, or when administered following either a single or five weekly subcutaneous administrations of 300 mg of COSENTYX [see Drug Interactions (7)].

Pharmacokinetics Following Intravenous Administration

Following an intravenous administration of 1.75 mg/kg maintenance dose every four weeks, with or without a loading dose of 6 mg/kg at Day 0, the secukinumab concentrations [steady state trough secukinumab concentrations (Cmin,ss), mean secukinumab concentrations (Cavg,ss), and maximum secukinumab concentrations (Cmax,ss)] are estimated to be within the range of the steady state concentrations following subcutaneous administration of 150 mg and 300 mg doses of COSENTYX administered every four weeks.

12.6 Immunogenicity

The observed incidence of anti-drug antibodies is highly dependent on the sensitivity and specificity of the assay. Differences in assay methods preclude meaningful comparisons of the incidence of anti-drug antibodies (ADA) in the trials described below with the incidence of ADA in other trials, including those of COSENTYX (secukinumab).

The immunogenicity of COSENTYX was evaluated using an electrochemiluminescence-based bridging immunoassay. Less than 1% of subjects treated with COSENTYX developed antibodies to secukinumab in up to 52 weeks of treatment. However, this assay has limitations in detecting anti-secukinumab antibodies in the presence of secukinumab; therefore, the incidence of antibody development might not have been reliably determined.

In up to 52 weeks of treatment in controlled trials in patients with PsO, PsA, AS, nr-axSpA, HS, pediatric PsO, JPsA and ERA [see Clinical Studies (14)], the incidence of anti-secukinumab antibodies (referred as ADA) formation was less than 1% (25 of 6268 total of subjects treated with COSENTYX). Of the subjects treated with COSENTYX who developed ADA, approximately 8% developed neutralizing antibodies. Because of the low occurrence of ADA, the effect of these antibodies on pharmacokinetics, pharmacodynamics, safety, or effectiveness of COSENTYX is unknown.

13 NONCLINICAL TOXICOLOGY

13.1 Carcinogenesis, Mutagenesis, Impairment of Fertility

Animal studies have not been conducted to evaluate the carcinogenic or mutagenic potential of COSENTYX. Some published literature suggests that IL-17A directly promotes cancer cell invasion in vitro, whereas other reports indicate IL-17A promotes T-cell mediated tumor rejection. Depletion of IL-17A with a neutralizing antibody inhibited tumor development in mice. The relevance of experimental findings in mouse models for malignancy risk in humans is unknown.

No effects on fertility were observed in male and female mice that were administered a murine analog of secukinumab at subcutaneous doses up to 150 mg/kg once weekly prior to and during the mating period.

14 CLINICAL STUDIES

14.1 Adult Plaque Psoriasis

Four multicenter, randomized, double-blind, placebo-controlled trials of subcutaneous COSENTYX (Trials PsO1, PsO2, PsO3, and PsO4) enrolled 2,403 subjects (691 randomized to COSENTYX 300 mg, 692 to COSENTYX 150 mg, 694 to placebo, and 323 to a biologic active control) 18 years of age and older with PsO who had a minimum BSA involvement of 10%, and Psoriasis Area and Severity Index (PASI) score greater than or equal to 12, and who were candidates for phototherapy or systemic therapy. In these studies, each 300 mg dose was administered as two injections of 150 mg.

- Trial PsO1 (NCT01365455) enrolled 738 subjects (245 randomized to COSENTYX 300 mg, 245 to COSENTYX 150 mg, and 248 to placebo). Subjects received subcutaneous treatment at Weeks 0, 1, 2, 3, and 4 followed by dosing every 4 weeks. Subjects randomized to receive placebo that were non-responders at Week 12 were crossed over to receive COSENTYX (either 300 mg or 150 mg) at Weeks 12, 13, 14, 15, and 16 followed by the same dose every 4 weeks. All subjects were followed for up to 52 weeks following first administration of trial treatment.
- Trial PsO2 (NCT01358578) enrolled 1306 subjects (327 randomized to COSENTYX 300 mg, 327 to COSENTYX 150 mg, 326 to placebo, and 323 to a biologic active control). Subjects received subcutaneous treatment at Weeks 0, 1, 2, 3, and 4 followed by dosing every 4 weeks. Subjects randomized to receive placebo that were non-responders at Week 12 crossed over to receive COSENTYX (either 300 mg or 150 mg) at Weeks 12, 13, 14, 15, and 16 followed by the same dose every 4 weeks. All subjects were followed for up to 52 weeks following first administration of trial treatment.
- Trial PsO3 (NCT01555125) enrolled 177 subjects (59 randomized to COSENTYX 300 mg, 59 to COSENTYX 150 mg, and 59 to placebo) and assessed safety, tolerability, and usability of COSENTYX self-administration via prefilled syringe for 12 weeks. Subjects received subcutaneous treatment at Weeks 0, 1, 2, 3, and 4, followed by the same dose every 4 weeks for up to 12 weeks total.
- Trial PsO4 (NCT01636687) enrolled 182 subjects (60 randomized to COSENTYX 300 mg, 61 to COSENTYX 150 mg, and 61 to placebo) and assessed safety, tolerability, and usability of COSENTYX self-administration via Sensoready pen for 12 weeks. Subjects received subcutaneous treatment at Weeks 0, 1, 2, 3, and 4, followed by the same dose every 4 weeks for up to 12 weeks total.

Endpoints

In all trials, the endpoints were the proportion of subjects who achieved a reduction in PASI score of at least 75% (PASI 75) from baseline to Week 12 and treatment success (clear or almost clear) on the Investigator’s Global Assessment modified 2011 (IGA). Other evaluated outcomes included the proportion of subjects who achieved a reduction in PASI score of at least 90% (PASI 90) from baseline at Week 12, maintenance of efficacy to Week 52, and improvements in itching, pain, and scaling at Week 12 based on the Psoriasis Symptom Diary©.

The PASI is a composite score that takes into consideration both the percentage of BSA affected and the nature and severity of psoriatic changes within the affected regions (induration, erythema, and scaling). The IGA is a 5-category scale, including “0 = clear”, “1 = almost clear”, “2 = mild”, “3 = moderate” or “4 = severe” indicating the physician’s overall assessment of the psoriasis severity focusing on induration, erythema, and scaling. Treatment success of “clear” or “almost clear” consisted of no signs of psoriasis or normal to pink coloration of lesions, no thickening of the plaque, and none to minimal focal scaling.

Baseline Disease Characteristics

Across all treatment groups, the baseline PASI score ranged from 11 to 72 with a median of 20 and the baseline IGA score ranged from “moderate” (62%) to “severe” (38%). Of the 2,077 PsO subjects who were included in the placebo-controlled trials, 79% were biologic-naïve (have never received a prior treatment with biologics) and 45% were non-biologic failures (failed to respond to a prior treatment with non-biologic therapies). Of the subjects who received a prior treatment with biologics, over one-third were biologic failures. Approximately 15% to 25% of trial subjects had a history of psoriatic arthritis.

Clinical Response

The results of Trials PsO1 and PsO2 are presented in Table 3.

Table 3: Clinical Outcomes at Week 12 in Adults With PsO in Trials PsO1 and PsO2 (Subcutaneous Treatment)
 | Trial PsO1 |  |  | Trial PsO2
 | COSENTYX 300 mg (N = 245) n (%) | COSENTYX 150 mg (N = 245) n (%) | Placebo (N = 248) n (%) | COSENTYX 300 mg (N = 327) n (%) | COSENTYX 150 mg (N = 327) n (%) | Placebo (N = 326) n (%)
PASI 75 response | 200 (82) | 174 (71) | 11 (4) | 249 (76) | 219 (67) | 16 (5)
IGA of clear or almost clear | 160 (65) | 125 (51) | 6 (2) | 202 (62) | 167 (51) | 9 (3)

The results of Trials PsO3 and PsO4 are presented in Table 4.

Table 4: Clinical Outcomes at Week 12 in Adults With PsO in Trials PsO3 and PsO4 (Subcutaneous Treatment)
 | Trial PsO3 |  |  | Trial PsO4
 | COSENTYX 300 mg (N = 59) n (%) | COSENTYX 150 mg (N = 59) n (%) | Placebo (N = 59) n (%) | COSENTYX 300 mg (N = 60) n (%) | COSENTYX 150 mg (N = 61) n (%) | Placebo (N = 61) n (%)
PASI 75 response | 44 (75) | 41 (69) | 0 (0) | 52 (87) | 43 (70) | 2 (3)
IGA of clear or almost clear | 40 (68) | 31 (53) | 0 (0) | 44 (73) | 32 (52) | 0 (0)

Examination of age, sex, and racial subgroups did not identify differences in response to COSENTYX among these subgroups. Based on post-hoc subgroup analyses in subjects with moderate to severe PsO, subjects with lower body weight and lower disease severity may achieve an acceptable response with COSENTYX 150 mg.

PASI 90 response at Week 12 was achieved with COSENTYX 300 mg and 150 mg compared to placebo in 59% (145/245) and 39% (95/245) versus 1% (3/248) of subjects, respectively (Trial PsO1) and 54% (175/327) and 42% (137/327) versus 2% (5/326) of subjects, respectively (Trial PsO2). Similar results were seen in Trials PsO3 and PsO4.

- With continued treatment over 52 weeks, subjects in Trial PsO1 who were PASI 75 responders at Week 12 maintained their responses in 81% (161/200) of the subjects treated with COSENTYX 300 mg and in 72% (126/174) of subjects treated with COSENTYX 150 mg. Trial PsO1 subjects who were clear or almost clear on the IGA at Week 12 also maintained their responses in 74% (119/160) of subjects treated with COSENTYX 300 mg and in 59% (74/125) of subjects treated with COSENTYX 150 mg.
- Similarly in Trial PsO2, PASI 75 responders maintained their responses in 84% (210/249) of subjects treated with COSENTYX 300 mg and in 82% (180/219) of subjects treated with COSENTYX 150 mg. Trial PsO2 subjects who were clear or almost clear on the IGA also maintained their responses in 80% (161/202) of subjects treated with COSENTYX 300 mg and in 68% (113/167) of subjects treated with COSENTYX 150 mg.

Among the subjects who chose to participate (39%) in assessments of patient reported outcomes, improvements in signs and symptoms related to itching, pain, and scaling at Week 12 compared to placebo (Trials PsO1 and PsO2) were observed using the Psoriasis Symptom Diary©.

Psoriasis Lesions of Scalp

A randomized, placebo-controlled trial (Trial PsO5; NCT02267135) enrolled 102 subjects with moderate to severe psoriasis lesions of scalp, defined as having a Psoriasis Scalp Severity Index (PSSI) score of greater than or equal to 12, an IGA scalp only score of 3 or greater, and at least 30% of the scalp affected. In this trial, 62% of subjects had at least 50% of scalp surface area affected. In this study, each 300 mg dose was administered as two injections of 150 mg. The proportions of subjects achieving an IGA scalp only score of 0 or 1 (clear or almost clear) were 56.9% and 5.9% for the COSENTYX 300 mg and the placebo groups, respectively.

300 mg/2 mL Pre-filled Syringe and 300 mg/2 mL UnoReady Pen

Two randomized, double-blind, placebo-controlled, 52-week trials (PsO6 and PsO7) enrolled 336 subjects at least 18 years of age with moderate to severe PsO who are candidates for systemic therapy or phototherapy to evaluate the safety and efficacy of COSENTYX 300 mg subcutaneously administered with a single 300 mg/2 mL prefilled syringe (Trial PsO6, NCT02748863, 214 patients) or with a single 300 mg/2 mL UnoReady pen (Trial PsO7, NCT03589885, 122 patients) compared to two subcutaneous injections using a 150 mg/1 mL prefilled syringe. The co-primary endpoints for both trials were the proportion of subjects who achieved a PASI 75 response and IGA mod 2011 ‘clear’ or ‘almost clear’ response with at least a two-grade reduction from baseline at Week 12.

Table 5: Clinical Outcomes at Week 12 in Adults With PsO in Trials PsO6 and PsO7 (Subcutaneous Treatment)
 | Trial PsO6 |  |  | Trial PsO7
 | COSENTYX 300 mg |  |  | COSENTYX 300 mg
 | 2 mL PFS (N = 72) % | Two 1 mL PFS (N = 71) % | Placebo (N = 71) % | 2 mL Pen (N = 41) % | Two 1 mL PFS (N = 41) % | Placebo (N = 40) %
IGA of clear or almost clear | 76 | 69 | 1 | 76 | 68 | 8
PASI 75 response | 89 | 82 | 2 | 95 | 83 | 10
PASI 90 response | 67 | 70 | 2 | 76 | 62 | 5
Abbreviation: PFS, prefilled syringe.
Missing data was imputed using multiple imputation.

14.2 Pediatric Plaque Psoriasis

A 52-week, multicenter randomized, double-blind, placebo and active-controlled trial (Trial PsO8; NCT02471144) enrolled 162 pediatric subjects 6 years of age and older, with severe plaque psoriasis (as defined by a PASI score ≥ 20, an IGA modified 2011 score of 4, and involving ≥ 10% of the BSA) who were candidates for systemic therapy.

Subjects were randomized to receive subcutaneous placebo, COSENTYX, or a biologic active control. In the COSENTYX groups, subjects with BW less than 25 kg received 75 mg, subjects with BW 25 to less than 50 kg received either 75 mg or 150 mg (2 times the recommended dose), and subjects with BW at least 50 kg received either 150 mg or 300 mg (2 times the recommended dose). In this study, each 300 mg dose was administered as two subcutaneous injections of 150 mg. Subjects in the COSENTYX and placebo groups received subcutaneous treatment at Weeks 0, 1, 2, 3, and 4 followed by dosing every 4 weeks. At Week 12, subjects randomized to placebo who were non-responders were switched to COSENTYX (dose based on body weight) and received COSENTYX at Weeks 12, 13, 14, and 15, followed by the same dose every 4 weeks starting at Week 16.

Baseline Characteristics

Overall, 60% of the subjects were female, 83% were White, the median BW was 50.6 kg, and the mean age was 13.5 years with 23% of the subjects less than 12 years. At baseline, the median PASI score was 26 (ranged from 17 to 60), and 99% of the subjects had an IGA modified 2011 score of 4 (‘severe’). Approximately 43% of the subjects had prior exposure to phototherapy, 53% to conventional systemic therapy, 3% to biologics, and 9% had concomitant psoriatic arthritis.

Endpoints

The co-primary endpoints were the proportion of subjects who achieved a reduction in PASI score of at least 75% (PASI 75) from baseline to Week 12 and the proportion of subjects who achieved an IGA modified 2011 score of ‘clear’ or ‘almost clear’ (0 or 1) with at least a 2-point improvement from baseline to Week 12. The key secondary endpoint was the proportion of subjects who achieved a reduction in PASI score of at least 90% (PASI 90) from baseline to Week 12.

Clinical Response

Table 6 presents the efficacy results at Week 12 by baseline weight strata for the approved dosage in Trial PsO8.

Table 6: Clinical Outcomes at Week 12 in Pediatric Subjects With Severe PsO in Trial PsO8 (Subcutaneous Treatment)
 | Body weight < 50 kg |  | Body weight ≥ 50 kg |  | Total
 | COSENTYX 75 mg (N = 22) n (%) | Placebo (N = 20) n (%) | COSENTYX 150 mg (N = 21) n (%) | Placebo (N = 21) n (%) | COSENTYXa (N = 43) n (%) | Placebo (N = 41) n (%)
IGA of clear or almost clear | 7 (32) | 1 (5) | 17 (81) | 1 (5) | 24 (56) | 2 (5)
PASI 75 response | 12 (55) | 2 (10) | 18 (86) | 4 (19) | 30 (70) | 6 (15)
PASI 90 response | 9 (41) | 1 (5) | 17 (81) | 0 (0) | 26 (60) | 1 (2)
Non-responder imputation was used to handle missing values.
aCOSENTYX treated subjects received 75 mg for subjects less than 50 kg and 150 mg for subjects at least 50 kg body weight.

14.3 Adult Psoriatic Arthritis

The safety and efficacy of COSENTYX were assessed in 1,999 patients, in 3 randomized, double-blind, placebo-controlled trials (PsA1, PsA2, and PsA3) in adult patients, age 18 years and older with active PsA (greater than or equal to 3 swollen and greater than or equal to 3 tender joints) despite non-steroidal anti-inflammatory drug (NSAID), corticosteroid or disease modifying anti-rheumatic drug (DMARD) therapy. Patients in these trials had a diagnosis of PsA of at least 5 years across all trials.

- PsA1 Study (NCT 01752634) evaluated 397 patients, who were treated with 75 mg, 150 mg or 300 mg of COSENTYX (administered as two subcutaneous injections of 150 mg) at Weeks 0, 1, 2, 3, and 4, followed by the same subcutaneous dose every 4 weeks. Patients who received placebo were re-randomized to receive subcutaneous COSENTYX (either 150 mg or 300 mg every 4 weeks) at Week 16 or Week 24 based on responder status. The primary endpoint was the percentage of patients achieving an ACR20 response at Week 24.
- PsA2 Study (NCT 01392326) evaluated 606 patients, who were treated with intravenous secukinumab 10 mg/kg, or placebo at Weeks 0, 2, and 4, followed by either 75 mg or 150 mg of subcutaneous COSENTYX treatment (or placebo) every 4 weeks. Patients who received placebo were re-randomized to receive subcutaneous COSENTYX (either 75 mg or 150 mg every 4 weeks) at Week 16 or Week 24 based on responder status.
- PsA3 Study (NCT 02404350) evaluated 996 patients, who were treated with 150 mg or 300 mg of COSENTYX (administered as two subcutaneous injections of 150 mg) at Weeks 0, 1, 2, 3, and 4 followed by the same subcutaneous dose every 4 weeks, or once every 4 weeks of COSENTYX 150 mg. Patients treated with placebo received subcutaneous COSENTYX, either 150 mg or 300 mg, per baseline randomization, at Week 16 or Week 24 based upon responder status. The primary endpoint was ACR20 response at Week 16 with the key secondary endpoint the change from baseline in modified Total Sharp Score (mTSS) at Week 24.

Baseline Disease Characteristics

At baseline, over 61% and 42% of the patients had enthesitis and dactylitis, respectively. Overall, 31% of patients discontinued previous treatment with anti-TNFα agents due to either lack of efficacy or intolerance. In addition, approximately 53% of patients from both studies had concomitant methotrexate (MTX) use. Patients with different subtypes of PsA were enrolled, including polyarticular arthritis with no evidence of rheumatoid nodules (80%), asymmetric peripheral arthritis (63%), distal interphalangeal involvement (58%), spondylitis with peripheral arthritis (20%), and arthritis mutilans (7%).

Clinical Response

In PsA1, patients treated with 150 mg or 300 mg COSENTYX demonstrated a greater clinical response, including ACR20, ACR50, and ACR70 compared to patients treated with placebo at Week 24 (Table 7). Responses were similar in patients regardless of concomitant MTX treatment. Responses were seen regardless of prior anti-TNFα exposure.

In patients with coexistent PsO receiving COSENTYX (n = 99), the skin lesions of psoriasis improved with treatment, relative to placebo, as measured by the Psoriasis Area Severity Index (PASI).

Table 7: Responsesa in PsA1 Study at Week 16 and Week 24 (Subcutaneous Treatment)
 | COSENTYX | COSENTYX | Placebo | Difference from placebo (95% CI)
 | 150 mg (N = 100) | 300 mg (N = 100) | (N = 98) | COSENTYX 150 mg | COSENTYX 300 mg
ACR20 response
Week 16 (%) | 60 | 57 | 18 | 42 (30, 54) | 38 (26, 51)
Week 24 (%) | 51 | 54 | 15 | 36 (24, 48) | 39 (27, 51)
ACR50 response
Week 16 (%) | 37 | 35 | 6 | 31 (21, 42) | 28 (18, 39)
Week 24 (%) | 35 | 35 | 7 | 28 (18, 38) | 28 (17, 38)
ACR70 response
Week 16 (%) | 17 | 15 | 2 | 15 (7, 23) | 13 (5, 20)
Week 24 (%) | 21 | 20 | 1 | 20 (12, 28) | 19 (11, 27)
aPatients who met escape criteria (less than 20% improvement in tender or swollen joint counts) at Week 16 were considered non-responders.

The percentage of patients who achieved a ACR20 response by visit is shown in Figure 1. Patients on placebo who received COSENTYX without a loading regimen achieved similar ACR20 responses over time (data not shown).

Figure 1: Percent of Adult Patients Who Achieved ACR 20 Responsea in PsA1 Study Through Week 24 (Subcutaneous Treatment)

aPatients who met escape criteria (less than 20% improvement in tender or swollen joint counts) at Week 16 were considered non-responders.

The improvements in the components of the ACR response criteria in the PsA1 study are shown in Table 8.

Table 8: Mean Change From Baseline in ACR Components at Week 16a (PsA1 Study) (Subcutaneous Treatment)
 | COSENTYX 150 mg (N = 100) | COSENTYX 300 mg (N = 100) | Placebo (N = 98)
Number of swollen joints
Baseline | 12.0 | 11.2 | 12.1
Mean change at Week 16 | -4.86 | -5.83 | -3.22
Number of tender joints
Baseline | 24.1 | 20.2 | 23.5
Mean change at Week 16 | -10.70 | -10.01 | -1.77
Patient’s assessment of pain
Baseline | 58.9 | 57.7 | 55.4
Mean change at Week 16 | -22.91 | -23.97 | -7.98
Patient global assessment
Baseline | 62.0 | 60.7 | 57.6
Mean change at Week 16 | -25.47 | -25.40 | -8.25
Physician global assessment
Baseline | 56.7 | 55.0 | 55.0
Mean change at Week 16 | -29.24 | -34.71 | -14.95
Disability index (HAQ)
Baseline | 1.2200 | 1.2828 | 1.1684
Mean change at Week 16 | -0.45 | -0.55 | -0.23
CRP (mg/L)
Baseline | 14.15 | 10.88 | 7.87
Mean change at Week 16b | -8.41 | -7.21 | 0.79
aWeek 16 rather than Week 24 data are displayed to provide comparison between arms prior to placebo escape to COSENTYX.
bMean change based upon observed data.

Improvements in enthesitis and dactylitis scores were observed in each COSENTYX group compared to placebo at Week 24.

Radiographic Response

In PsA3 Study, inhibition of progression of structural damage was assessed radiographically and expressed by the modified mTSS and its components, the Erosion Score (ES) and Joint Space Narrowing Score (JSN), at Week 24 compared to baseline. Radiographs of hands, wrists, and feet were obtained at baseline, Week 16 and/or Week 24 and scored independently by at least two readers who were blinded to treatment group and visit number. Treatment with subcutaneous COSENTYX 150 mg without a loading dose, 150 mg with a loading dose and 300 mg with a loading dose significantly inhibited progression of peripheral joint damage compared with treatment with placebo as measured by change from baseline in mTSS at Week 24. The percentage of patients with no disease progression (defined as a change from baseline in mTSS of less than or equal to 0.0) from randomization to Week 24 was 75.7%, 70.9%, and 76.5% for COSENTYX 150 mg without a loading dose, 150 mg, 300 mg, respectively versus 68.2% for placebo.

Table 9: Rate of Change per 24 Weeks in Modified Total Sharp Score (Subcutaneous Treatment)
Treatment | N | Rate of change per 24 weeks | Difference from placebo (95% CI)
COSENTYX 150 mg without a loading dose | 210 | -0.10 | -0.61 (-0.95, -0.26)
COSENTYX 150 mg with a loading dose | 213 | 0.14 | -0.37 (-0.71, -0.03)
COSENTYX 300 mg with a loading dose | 217 | 0.03 | -0.48 (-0.82, -0.14)
Placebo | 296 | 0.51 | --
Results from a linear mixed effects model that excluded data after escape for placebo subjects who received escape therapy at Week 16. The model assumes approximately linear progression over time and estimates a difference in rates (slopes) of progression over 24 weeks to compare treatment arms.

Physical Function

Improvement in physical function as assessed by Health Assessment Questionnaire-Disability Index (HAQ-DI) demonstrated that the proportion of patients who achieved at least -0.3 improvement in HAQ-DI score from baseline was greater in the subcutaneous COSENTYX 150 mg and 300 mg groups compared to the placebo group at Weeks 16 and 24. At Week 16 in PsA1 study, estimated mean change from baseline was -0.23 in the placebo group compared with -0.45 in the COSENTYX 150 mg group and -0.55 in the COSENTYX 300 mg group.

Treatment of Adult Patients with Active Psoriatic Arthritis with Intravenous COSENTYX

The effectiveness of intravenous COSENTYX in the treatment of adult patients with active PsA was extrapolated from the established effectiveness of subcutaneous COSENTYX in adult patients with active PsA based on pharmacokinetic exposure [see Clinical Pharmacology (12.3)].

14.4 Ankylosing Spondylitis

The safety and efficacy of subcutaneous COSENTYX were assessed in 816 adult patients (18 years of age and older) with active AS in three randomized, double-blind, placebo-controlled trials (AS1, AS2, and AS3). Patients had active disease as defined by the Bath Ankylosing Spondylitis Disease Activity Index (BASDAI) greater or equal to 4 despite non-steroidal anti-inflammatory drug (NSAID), corticosteroid or disease modifying anti-rheumatic drug (DMARD) therapy.

- AS1 Study (NCT01649375) evaluated 219 patients, who were treated with 75 mg or 150 mg of subcutaneous COSENTYX treatment at Weeks 0, 1, 2, 3, and 4, followed by the same dose every 4 weeks. At Week 16, patients who received placebo were re-randomized to either 75 mg or 150 mg of subcutaneous COSENTYX every 4 weeks. The primary endpoint was the percentage of patients who achieved an ASAS20 response at Week 16.
- AS2 Study (NCT01358175) evaluated 371 patients, who were treated with intravenous secukinumab 10 mg/kg at Weeks 0, 2, and 4 (for both treatment arms) or placebo, followed by either 75 mg or 150 mg subcutaneous COSENTYX treatment every 4 weeks or placebo. Patients who received placebo were re-randomized to receive subcutaneous COSENTYX (either 75 mg or 150 mg every 4 weeks) at Week 16 or Week 24 based on responder status.
- AS3 Study (NCT02008916) evaluated 226 patients, who were treated with intravenous secukinumab 10 mg/kg at Weeks 0, 2, and 4 (for both treatment arms) or placebo, followed by either 150 mg or 300 mg subcutaneous COSENTYX treatment every 4 weeks or placebo. Patients who received placebo were re-randomized to receive subcutaneous COSENTYX (either 150 mg or 300 mg every 4 weeks) at Week 16. The primary endpoint was the percentage of patients who achieved an ASAS20 response at Week 16. Patients were blinded to the treatment regimen up to Week 52, and the trial continued to Week 156. In this study, each 300 mg dose was administered as two injections of 150 mg.

Baseline Disease Characteristics

At baseline, approximately 13% and 25% used concomitant MTX or sulfasalazine, respectively. Overall, 29% of patients discontinued previous treatment with anti-TNFα agents due to either lack of efficacy or intolerance.

Clinical Response

In AS1, patients treated with 150 mg COSENTYX demonstrated greater improvements in ASAS20 and ASAS40 responses compared to patients treated with placebo at Week 16 (Table 10). Responses were similar in patients regardless of concomitant therapies.

Table 10: ASAS20 and ASAS40 Responses in All AS Patients at Week 16 in Study AS1 (Subcutaneous Treatment)
 | COSENTYX 150 mg (n = 72) | Placebo (n = 74) | Difference from placebo (95% CI)
ASAS20 response, % | 61 | 28 | 33 (18, 48)
ASAS40 response, % | 36 | 11 | 25 (12, 38)

The improvements in the main components of the ASAS20 response criteria and other measures of disease activity are shown in Table 11.

Table 11: ASAS20 Components and Other Measures of Disease Activity at Week 16 (AS1 Study) (Subcutaneous Treatment)
 | COSENTYX 150 mg (N = 72) |  | Placebo (N = 74)
 | Baseline | Week 16 change from baseline | Baseline | Week 16 change from baseline
ASAS20 response criteria
-Patient Global Assessment of Disease Activity (0-100 mm)^1 | 67.5 | -27.7 | 70.5 | -12.9
-Total spinal pain (0-100 mm) | 66.2 | -28.5 | 69.2 | -10.9
-BASFI (0-10)^2 | 6.2 | -2.2 | 6.1 | -0.7
-Inflammation (0-10)^3 | 6.5 | -2.5 | 6.5 | -0.8
BASDAI score^4 | 6.6 | -2.2 | 6.8 | -0.9
BASMI^5 | 3.6 | -0.51 | 3.9 | -0.22
hsCRP^6 (mg/L) mean change at Week 16 | 27.0 | -17.2 | 15.9 | 0.8
1. Percent of subjects with at least a 20%- and 10-unit improvement measured on a Visual Analog Scale (VAS) with 0 = none, 100 = severe.
2. Bath Ankylosing Spondylitis Functional Index.
3. Inflammation is the mean of two patient-reported stiffness self-assessments in BASDAI.
4. Bath Ankylosing Spondylitis Disease Activity Index.
5. Bath Ankylosing Spondylitis Metrology Index.
6. High sensitivity C-reactive protein / mean change based upon observed data.

The percentage of patients who achieved ASAS20 responses by visit is shown in Figure 2. Patients on placebo who received COSENTYX without a loading regimen achieved similar ASAS20 responses over time (data not shown).

Figure 2: ASAS20 Responses in All AS1 Study Patients Over Time Up to Week 16 (Subcutaneous Treatment)

In AS3 Study, patients treated with subcutaneous COSENTYX (150 mg and 300 mg) demonstrated improved signs and symptoms, and had comparable efficacy responses, regardless of dose, that were superior to placebo at Week 16 for the primary and most secondary endpoints. At Week 16, the ASAS20 and ASAS40 responses were 58.1% and 40.5% for 150 mg and 60.5% and 42.1% for 300 mg, respectively. The percent of patients achieving ASAS20 responses by visit is shown in Figure 3.

COSENTYX treated patients showed improvement compared to placebo-treated patients in health-related quality of life as assessed by ASQoL at Week 16.

Figure 3: ASAS20 Responses in All AS3 Study Patients Over Time Up to Week 16 (Subcutaneous Treatment)

Treatment of Adult Patients with Active Ankylosing Spondylitis with Intravenous COSENTYX

The effectiveness of intravenous COSENTYX in the treatment of adult patients with active AS was extrapolated from the established effectiveness of subcutaneous COSENTYX in adult patients with active AS based on pharmacokinetic exposure [see Clinical Pharmacology (12.3)].

14.5 Non-Radiographic Axial Spondyloarthritis

The safety and efficacy of COSENTYX were assessed in 555 adult patients (18 years of age and older) with active nr-axSpA in one randomized, double-blind, placebo-controlled Phase 3 study (nr-axSpA1, NCT02696031). Patients met ASAS criteria for axSpA with objective signs of inflammation and had active disease as defined by a BASDAI greater or equal to 4, a Visual Analogue Scale (VAS) for total back pain greater or equal to 40 (on a scale of 0-100 mm) despite NSAID therapy and no evidence of radiographic changes in the sacroiliac joints that would meet the modified New York criteria for AS. Patients also had to have objective signs of inflammation with a C-reactive protein (CRP) level above the upper limit of normal and/or evidence of sacroiliitis on Magnetic Resonance Imaging (MRI).

Patients were treated with 150 mg of subcutaneous COSENTYX treatment with a loading dosage (Weeks 0, 1, 2, 3, and 4) or without a loading dosage (Weeks 0 and 4) followed by the same dose every 4 weeks or placebo. In the double-blind period, patients (n = 555) received either placebo or COSENTYX for 52 weeks. Starting Week 16, dosage adjustment or addition of concomitant NSAIDs and DMARDs was permitted. Starting at Week 20, patients were allowed to switch to open-label 150 mg of subcutaneous COSENTYX monthly or other biologic at the discretion of the investigator and patient. The primary endpoint was at least 40% improvement in Assessment of Spondyloarthritis International Society (ASAS40) at Week 52.

Baseline Disease Characteristics

Approximately 10% and 15% of patients used concomitant MTX or sulfasalazine, respectively. Overall, 10% of patients had received previous treatment with anti-TNFα agents and discontinued these due to either lack of efficacy or intolerance.

Clinical Response

In nr-axSpA1 Study, treatment with COSENTYX 150 mg resulted in significant improvements in the measure of disease activity compared to treatment with placebo at Week 16 and Week 52 (Table 12).

Table 12: Clinical Response in the nr-axSpA1 Study at Week 16 and Week 52 (Subcutaneous Treatment)
Number of subjects with ASAS40 response (%) | COSENTYX 150 mg without load (n = 184) | COSENTYX 150 mg with load (n = 185) |  | Difference from placebo (95% CI)
 |  |  | Placebo (n = 186) | COSENTYX 150 mg without load | COSENTYX 150 mg with load
Week 16 | 75 (41) | 74 (40) | 52 (28) | 13 (3, 22) | 12 (2, 22)
Week 52 | 70 (38) | 62 (34) | 36 (19) | 19 (10, 28) | 14 (5, 23)
Difference in proportions with 95% CI based on normal approximation.

The results of the main components of the ASAS40 response criteria in the nr-axSpA1 Study are shown in Table 13.

Table 13: Main Components of the ASAS40 Response Criteria and Other Measures of Disease Activity in nr-axSpA Patients at Baseline and Week 16 in the nr-axSpA1 Study (Subcutaneous Treatment)
 | COSENTYX 150 mg without loading dosage (N = 184) |  | COSENTYX 150 mg with a loading dosage (N = 185) |  | Placebo (N = 186)
 | Baseline | Week 16 change from baseline | Baseline | Week 16 change from baseline | Baseline | Week 16 change from baseline
ASAS40 response criteria
-Patient Global Assessment of Disease Activity (0-100 mm) | 71.0 | -26.2 | 72.6 | -24.1 | 68.8 | -13.8
-Total back pain (0-100 mm) | 72.0 | -25.5 | 73.3 | -25.0 | 70.9 | -15.6
-BASFI (0-10) | 5.9 | -1.6 | 6.2 | -1.8 | 5.9 | -1.0
-Inflammation (0-10) | 6.8 | -2.8 | 7.2 | -2.8 | 6.6 | -1.7
hsCRP (mg/L) mean change at Week 16 | 9.8 | -4.7 | 13.4 | -7.9 | 9.2 | -2.4
BASDAI (0-10) | 6.9 | -2.4 | 7.1 | -2.4 | 6.8 | -1.5
-Spinal pain | 7.6 | -3.0 | 7.8 | -3.0 | 7.5 | -2.0
-Peripheral pain and swelling (0-10) | 6.6 | -2.4 | 6.3 | -2.3 | 6.1 | -1.6
BASMI | 2.8 | -0.3 | 2.9 | -0.3 | 2.8 | -0.1

The percentage of patients achieving an ASAS40 response by visit is shown in Figure 4.

Figure 4: ASAS40 Responses in nr-axSpA1 Study Over Time up to Week 16 (Subcutaneous Treatment)

Health-Related Quality of Life

COSENTYX treated patients showed improvement in both loading and without loading dosage arms compared to placebo-treated patients at Week 16 in health-related quality of life as measured by ASQoL (LS mean change: Week 16: -3.5 and -3.6 versus -1.8, respectively).

Treatment of Adult Patients with Active Non-radiographic Axial Spondyloarthritis with Intravenous COSENTYX

The effectiveness of intravenous COSENTYX in the treatment of adult patients with active nr-axSpA was extrapolated from the established effectiveness of subcutaneous COSENTYX in adult patients with active nr-axSpA based on pharmacokinetic exposure [see Clinical Pharmacology (12.3)].

14.6 Juvenile Psoriatic Arthritis and Enthesitis-Related Arthritis

The efficacy and safety of subcutaneous secukinumab were assessed in a two-year, 3-part, double-blind, placebo-controlled, event-driven, randomized, Phase 3 study (NCT03031782) in 86 pediatric patients (2 to less than 18 years of age) with active ERA or JPsA as diagnosed based on a modified International League of Associations for Rheumatology (ILAR) Juvenile Idiopathic Arthritis (JIA) classification criteria. The trial consisted of an open-label portion (Part 1) followed by randomized withdrawal (Part 2) followed by open-label treatment (Part 3). Patients were given subcutaneous doses of 75 mg if they weighed less than 50 kg, or subcutaneous doses of 150 mg if they weighed at least 50 kg or greater, administered by subcutaneous injection at Weeks 0, 1, 2, 3, and 4, and every 4 weeks thereafter.

The primary endpoint was time to flare in Part 2. Disease flare was defined as at least 30% worsening in at least three of the six JIA ACR response criteria and at least 30% improvement in not more than one of the six JIA ACR response criteria and a minimum of two active joints.

In open-label Part 1, all patients received subcutaneous secukinumab until Week 12. Patients classified as responders (achieving JIA ACR30 response) at Week 12 entered into the Part 2 double-blind phase and were randomized 1:1 to continue treatment with secukinumab or begin treatment with placebo.

Baseline Disease Characteristics

The JIA patient subtypes at study entry were: 60.5% ERA and 39.5% JPsA. In the study, 67.6% of patients with JPsA, and 63.5% of patients with ERA, were treated concomitantly with MTX.

Clinical Response

Similar responses were seen in each JIA subtype (JPsA and ERA). The JIA ACR 30, 50, 70, and 90 responses for patients with JPsA and ERA at Week 12 are presented below in Table 14.

Table 14: JIA ACR 30, 50, 70, and 90 Responses at Week 12 (Subcutaneous Treatment)
Number of subjects with response (%) | JIA ACR 30 | JIA ACR 50 | JIA ACR 70 | JIA ACR 90
JPsA (N = 34) | 31 (91) | 31 (91) | 24 (71) | 16 (47)
ERA (N = 52) | 44 (85) | 41 (79) | 34 (65) | 17 (33)

Juvenile Psoriatic Arthritis Results

During Part 2, a total of 11 JPsA patients in the placebo group experienced a flare event compared with 4 JPsA patients in the secukinumab group. The risk of flare was reduced by 85% for patients who received secukinumab compared with patients who received placebo (Hazard Ratio = 0.15, 95% CI: 0.04 to 0.56) (Figure 5).

Figure 5: Kaplan-Meier Estimates of the Time to Disease Flare in Part 2 for JPsA Patients (Subcutaneous Treatment)

Enthesitis-Related Arthritis Results

During Part 2, a total of 10 ERA patients in the placebo group experienced a flare event compared with 6 ERA patients in the secukinumab group. The risk of flare was reduced by 53% for patients who received secukinumab compared with patients who received placebo (Hazard Ratio = 0.47, 95% CI: 0.17 to 1.32) (Figure 6). Supplementary analyses provided confirmatory evidence of the treatment effect in ERA.

Figure 6: Kaplan-Meier Estimates of the Time to Disease Flare in Part 2 for ERA Patients (Subcutaneous Treatment)

14.7 Hidradenitis Suppurativa

Two randomized, double-blind, placebo-controlled 52-week Phase 3 trials (i.e., HS Trial 1 [NCT03713619] and HS Trial 2 [NCT03713632]) assessed the efficacy and safety of COSENTYX in the treatment of adult patients with moderate to severe hidradenitis suppurativa (HS). In both trials, subjects were randomized to placebo or COSENTYX 300 mg by subcutaneous injection at Weeks 0, 1, 2, 3 and 4, followed by 300 mg every 2 weeks or every 4 weeks. At Week 16, subjects who were randomized to placebo were reassigned to receive COSENTYX 300 mg at Weeks 16, 17, 18, 19, and 20 followed by either COSENTYX 300 mg every 2 weeks (Q2W) or COSENTYX 300 mg every 4 weeks (Q4W).

Baseline Demographics and Disease Characteristics

HS Trials 1 and 2 included 1,084 adult subjects with moderate to severe HS. HS Trial 1 evaluated 541 subjects and HS Trial 2 evaluated 543 subjects, of whom 13% and 11%, respectively, received concomitant stable dose of systemic antibiotics. In HS Trial 1 and HS Trial 2, 24% and 23% of patients, respectively, were previously treated with a biologic (biologic-exposed patients) and discontinued the biologic agent for either lack of efficacy or intolerance.

Endpoints

The primary endpoint in both trials was the proportion of subjects who achieved a Hidradenitis Suppurativa Clinical Response (HiSCR50) defined as at least a 50% decrease in abscesses and inflammatory nodules (AN) count with no increase in the number of abscesses and/or in the number of draining fistulae relative to baseline at Week 16.

Clinical Response

In HS Trial 1 and HS Trial 2, a statistically significantly higher proportion of subjects treated with COSENTYX 300 mg every 2 weeks (after the first four weeks) achieved a HiSCR50 response at Week 16 compared to patients treated with placebo (see Table 15). In both HS trials, a higher proportion of subjects treated with COSENTYX 300 mg every 4 weeks (after the first four weeks) achieved HiSCR50 at Week 16 compared to subjects treated with placebo (see Table 15), where statistical significance was reached in HS Trial 2. In both trials, the onset of action of COSENTYX occurred as early as Week 2 and the efficacy progressively increased up to Week 16.

For the primary endpoint, HiSCR50, subjects who received any rescue medication or lesion intervention were considered treatment failures and handled as non-responders (n = 20 in Placebo, 11 in Q4W, and 8 in Q2W in HS Trial 1; n = 23 in Placebo, 17 in Q4W, and 13 in Q2W in HS Trial 2).

Improvements were seen for the primary endpoint in HS subjects regardless of previous or concomitant antibiotic treatment or previous biologic exposure.

Table 15: Clinical Response at Week 16 in Adults with Hidradenitis Suppurativa in HS Trial 1 and HS Trial 2^1
 | HS Trial 1 |  |  | HS Trial 2
 | Placebo (n = 180) | COSENTYX 300 mg every 4 weeks^2 (n = 180) | COSENTYX 300 mg every 2 weeks^2 (n = 181) | Placebo (n = 183) | COSENTYX 300 mg every 4 weeks^2 (n = 180) | COSENTYX 300 mg every 2 weeks^2 (n = 180)
HiSCR50 | 29.4% | 41.3% | 44.5%* | 26.1% | 42.5%* | 38.3%*
^1Multiple imputation was implemented for missing data.
^2Subjects received COSENTYX 300 mg by subcutaneous injection at Weeks 0, 1, 2, 3 and 4, followed by 300 mg every 4 weeks (Q4W) or every 2 weeks (Q2W).
*Statistically significant versus placebo based on the pre-defined hierarchy with overall alpha = 0.05 (two-sided).

16 HOW SUPPLIED/STORAGE AND HANDLING

How Supplied

COSENTYX (secukinumab) injection is a clear to opalescent, colorless to slightly yellowish solution available as follows:

COSENTYX injection for subcutaneous use

COSENTYX 300 mg/2 mL UnoReady pen

- NDC 0078-1070-68: Carton of one 300 mg/2 mL (300 mg dose) single-dose UnoReady pen (injection)

COSENTYX 300 mg/2 mL (150 mg/mL) prefilled syringe

- NDC 0078-1070-97: Carton of one 300 mg/2 mL (150 mg/mL) single-dose prefilled syringe (injection)

COSENTYX 150 mg/mL Sensoready pen

- NDC 0078-0639-41: Carton of two 150 mg/mL (300 mg dose) single-dose Sensoready pens (injection)
- NDC 0078-0639-68: Carton of one 150 mg/mL single-dose Sensoready pen (injection)

COSENTYX 150 mg/mL prefilled syringe

- NDC 0078-0639-98: Carton of two 150 mg/mL (300 mg dose) single-dose prefilled syringes (injection)
- NDC 0078-0639-97: Carton of one 150 mg/mL single-dose prefilled syringe (injection)

COSENTYX 75 mg/0.5 mL prefilled syringe (for pediatric patients less than 50 kg)

- NDC 0078-1056-97: Carton of one 75 mg/0.5 mL single-dose prefilled syringe (injection)

The removable cap of the COSENTYX 150 mg/mL Sensoready pen and prefilled syringe, and 75 mg/0.5 mL prefilled syringe contains natural rubber latex. Each 300 mg/2 mL UnoReady pen, 150 mg/mL Sensoready pen and 300 mg/2 mL, 150 mg/mL, and 75 mg/0.5 mL prefilled syringe is equipped with a needle safety guard.

COSENTYX injection for intravenous use

- NDC 0078-1168-61: Carton containing one 125 mg/5 mL (25 mg/mL) solution in a single-dose vial for dilution prior to intravenous infusion.

Storage and Handling

Refrigerate COSENTYX injection for subcutaneous use (300 mg/2 mL UnoReady Pen, 150 mg/mL Sensoready Pens, and 150 mg/mL and 75 mg/0.5 mL Prefilled Syringes), and COSENTYX injection for intravenous use at 2ºC to 8ºC (36ºF to 46ºF). Keep the products in the original carton to protect from light until the time of use. Do not freeze. To avoid foaming, do not shake. COSENTYX does not contain a preservative; discard any unused portion.

If removed from refrigeration, COSENTYX 150 mg/mL Sensoready Pens, and 150 mg/mL and 75 mg/0.5 mL Prefilled Syringes:

- May be stored for up to 4 days at room temperature not to exceed 30°C (86°F).
- Write the date COSENTYX is removed from and returned to the refrigerator in the space provided on the carton.
- Discard if stored outside of the refrigerator over 4 days.
- May be returned to the refrigerator only one time and must be stored at 2ºC to 8ºC (36ºF to 46ºF) until used or expired.

17 PATIENT COUNSELING INFORMATION

Advise the patient to read the FDA-approved patient labeling (Medication Guide and Instructions for Use).

Infections

Inform patients that COSENTYX may lower the ability of their immune system to fight infections and that serious infections, including opportunistic infections, may occur with the use of COSENTYX. Instruct patients of the importance of communicating any history of infections to the doctor and contacting their doctor if they develop any symptoms of infection [see Warnings and Precautions (5.1, 5.3)].

Hypersensitivity

Advise patients to seek immediate medical attention if they experience any symptoms of serious hypersensitivity reactions [see Warnings and Precautions (5.2)].

Eczematous Eruptions

Inform patients that skin reactions resembling eczema may occur with the use of COSENTYX. Instruct patients to seek medical advice if they develop signs or symptoms of eczema [see Warnings and Precautions (5.5)].

Risk of Hypersensitivity in Latex-Sensitive Individuals

Advise latex-sensitive patients that the removal caps of the COSENTYX 150 mg/mL Sensoready pen and the COSENTYX 1 mL and 0.5 mL prefilled syringes contain natural rubber latex, which may cause an allergic reaction in latex-sensitive individuals [see Warnings and Precautions (5.6)].

Immunization

Advise patients that vaccination with live vaccines is not recommended during COSENTYX treatment. Instruct patients to inform the healthcare practitioner that they are taking COSENTYX prior to a potential vaccination [see Warnings and Precautions (5.7)].

Instructions on Subcutaneous Injection Technique

If a patient or caregiver is to subcutaneously administer COSENTYX using the UnoReady pen, Sensoready pen, or the prefilled syringe, instruct him/her in injection techniques and assess their ability to inject subcutaneously to ensure the proper administration of COSENTYX [see Dosage and Administration (2.2, 2.9), Medication Guide, and Instructions for Use].

For pediatric patients, inform patients and caregivers that pediatric patients should not self-administer COSENTYX.

Instruct patients or caregivers in the technique of proper syringe and needle disposal and advise them not to reuse these items. Instruct patients to inject the full amount of COSENTYX according to the directions provided in the Medication Guide and Instructions for Use.

Storage

Instruct patients to store COSENTYX in a refrigerator at 2°C to 8°C (36ºF to 46ºF) and to discard expired or unused COSENTYX.

Inform patients that if removed from refrigeration, COSENTYX 150 mg/mL Sensoready pens, 150 mg/mL and 75 mg/0.5 mL prefilled syringes may be stored for up to 4 days at room temperature not to exceed 86°F (30°C). Instruct patients to discard if kept outside of the refrigerator over 4 days [see How Supplied/Storage and Handling (16)].

Manufactured by:
Novartis Pharmaceuticals Corporation
East Hanover, New Jersey 07936

US License Number 1244

© Novartis

T2025-48

MEDICATION GUIDE
COSENTYX® (koe-sen-tix)
(secukinumab)
injection, for subcutaneous or intravenous use

What is the most important information I should know about COSENTYX?
COSENTYX is a medicine that affects your immune system. COSENTYX may increase your risk of having serious side effects such as:
Infections. COSENTYX may lower the ability of your immune system to fight infections and may increase your risk of infections. Some people have had serious infections while taking COSENTYX, including tuberculosis (TB), and infections caused by bacteria, fungi, or viruses. Some people have died from these infections.

- Your healthcare provider should check you for TB before starting treatment with COSENTYX.
- If your healthcare provider feels that you are at risk for TB, you may be treated with medicine for TB before you begin treatment with COSENTYX and during treatment with COSENTYX.
- Your healthcare provider should watch you closely for signs and symptoms of TB during treatment with COSENTYX. Do not use COSENTYX if you have an active TB infection.

Before starting COSENTYX, tell your healthcare provider if you:

- are being treated for an infection
- have an infection that does not go away or that keeps coming back
- have TB or have been in close contact with someone with TB
- think you have an infection or have symptoms of an infection such as:

◦ fever, sweats, or chills
◦ muscle aches
◦ cough
◦ shortness of breath
◦ blood in your phlegm

◦ weight loss
◦ warm, red, or painful skin or sores on your body
◦ diarrhea or stomach pain
◦ burning when you urinate or urinate more often than normal

After starting COSENTYX, call your healthcare provider right away if you have any of the signs of infection listed above. Do not use COSENTYX if you have any signs of infection unless you are instructed to by your healthcare provider.
See “What are the possible side effects of COSENTYX?” for more information about side effects.

What is COSENTYX?
COSENTYX is a prescription medicine used to treat:

- people 6 years of age and older with moderate to severe plaque psoriasis (PsO) that involves large areas or many areas of the body, and who may benefit from taking injections or pills (systemic therapy) or phototherapy (treatment using ultraviolet or UV light alone or with systemic therapy)
- people 2 years of age and older with active psoriatic arthritis (PsA)
- adults with active ankylosing spondylitis (AS)
- adults with active non-radiographic axial spondyloarthritis (nr-axSpA) and objective signs of inflammation
- people 4 years of age and older with active enthesitis-related arthritis (ERA)
- adults with moderate to severe hidradenitis suppurativa (HS)

It is not known if COSENTYX is safe and effective in children:

- under 6 years of age with PsO
- under 2 years of age and weighing less than 33 pounds (15 kg) with active PsA
- under 4 years of age and weighing less than 33 pounds (15 kg) with active ERA
- with HS

Do not use COSENTYX if you:

- have had a severe allergic reaction to secukinumab or any of the other ingredients in COSENTYX. See the end of this Medication Guide for a complete list of ingredients in COSENTYX.

Before using COSENTYX, tell your healthcare provider about all of your medical conditions, including if you:

- have any of the conditions or symptoms listed in the section “What is the most important information I should know about COSENTYX?”
- have inflammatory bowel disease (Crohn’s disease or ulcerative colitis).
- are allergic to latex. The needle cap on the COSENTYX Sensoready pen, and 150 mg/mL and 75 mg/0.5 mL prefilled syringes contains latex.
- have recently received or are scheduled to receive an immunization (vaccine). People who take COSENTYX should not receive live vaccines. Children should be brought up to date with all vaccines before starting COSENTYX.
- are pregnant or plan to become pregnant. It is not known if COSENTYX can harm your unborn baby. You and your healthcare provider should decide if you will use COSENTYX.
- are breastfeeding or plan to breastfeed. It is not known if COSENTYX passes into your breast milk.

Tell your healthcare provider about all the medicines you take, including prescription and over-the-counter medicines, vitamins, and herbal supplements.
Know the medicines you take. Keep a list of your medicines to show your healthcare provider and pharmacist when you get a new medicine.

How will I receive COSENTYX?
When administered subcutaneously (under your skin)
Read the detailed “Instructions for Use” that comes with your COSENTYX for information on how to prepare and inject a dose of COSENTYX, and how to properly throw away (dispose of) used COSENTYX.

- Use COSENTYX exactly as prescribed by your healthcare provider.
- COSENTYX comes in a single-dose UnoReady pen, single-dose Sensoready pen, or single-dose prefilled syringes (300 mg/2 mL, 150 mg/mL, 75 mg/0.5 mL) that you or your caregiver may use at home to give injections.
- Your healthcare provider will decide which type of COSENTYX, and which dose is right for you.
- If your healthcare provider decides that you or a caregiver may give your injections of COSENTYX at home, you should receive training on the right way to prepare and inject COSENTYX. Do not try to inject COSENTYX yourself, until you or your caregiver has been shown how to inject COSENTYX by your healthcare provider.
- Children should not inject themselves with COSENTYX. An adult caregiver should prepare and inject COSENTYX after receiving training on the right way to prepare and inject COSENTYX.
- Do not handle the needle cap of the COSENTYX Sensoready pen, or the 75 mg/0.5 mL or 150 mg/mL prefilled syringes if you are sensitive to latex.
- COSENTYX is given as an injection under your skin (subcutaneous injection), in your upper legs (thighs) or stomach-area (abdomen) by you or a caregiver. A caregiver or healthcare provider may also give you an injection of COSENTYX in your upper outer arm.
- Do not give an injection in an area of the skin that is tender, bruised, red or hard, or in an area of skin that is affected by psoriasis.
- Each injection should be given at a different site. Do not use the 2-inch area around your navel (belly button).
- If you inject more COSENTYX than prescribed, call your healthcare provider or Poison Help line at 1-800-222-1222, or go to the nearest emergency room right away.

When administered intravenously (by vein)

- You will be given COSENTYX by a healthcare provider through a needle placed in a vein (infusion). It takes about 30 minutes to give you the full dose of COSENTYX.
- Your healthcare provider will tell you how often you should receive COSENTYX.
- If you miss an appointment to receive COSENTYX, make another appointment as soon as possible.

What are the possible side effects of COSENTYX?
COSENTYX may cause serious side effects, including:

- See “What is the most important information I should know about COSENTYX?”
- Serious allergic reactions. Get emergency medical help right away if you get any of the following symptoms of a serious allergic reaction:

◦ feel faint
◦ swelling of your face, eyelids, lips, mouth, tongue, or throat

◦ trouble breathing or throat tightness
◦ chest tightness

◦ skin rash
◦ hives (red, itchy bumps)

If you have a severe allergic reaction, do not give another injection of COSENTYX.

- Inflammatory bowel disease. New cases of inflammatory bowel disease or “flare-ups” can happen with COSENTYX and can sometimes be serious. If you have inflammatory bowel disease (ulcerative colitis or Crohn’s disease), tell your healthcare provider if you have worsening disease symptoms during treatment with COSENTYX or develop new symptoms of stomach pain or diarrhea.
- Severe skin reactions that look like eczema can happen during treatment with COSENTYX from days to months after your first dose and can sometimes lead to hospitalization. Your healthcare provider may temporarily stop treatment with COSENTYX if you develop severe skin reactions. Tell your healthcare provider if you have any of the following signs or symptoms:

◦ redness or rash
◦ itching
◦ small bumps or patches

◦ your skin is dry or feels like leather
◦ blisters on the hands or feet that ooze or become crusty
◦ skin peeling

The most common side effects of COSENTYX include:

• cold symptoms

• diarrhea

• upper respiratory tract infections

These are not all of the possible side effects of COSENTYX.
Call your doctor for medical advice about side effects. You may report side effects to FDA at 1-800-FDA-1088.

How should I store COSENTYX?

- Store COSENTYX in a refrigerator, between 36°F to 46°F (2°C to 8°C).
- Keep COSENTYX in the original carton until ready for use to protect from light.
- If you use COSENTYX Sensoready pen, or COSENTYX 75 mg/0.5 mL or 150 mg/mL prefilled syringe:
  - It may be stored at room temperature, up to 86°F (30°C), for up to 4 days.
  - Write the date it was removed from and returned to the refrigerator in the space provided on the carton.
  - Throw it away if it has been stored outside of the refrigerator over 4 days.
  - It may be returned to the refrigerator only 1 time and must be stored between 36°F to 46°F (2°C to 8°C) until you use it or until it expires.
- Do not freeze COSENTYX.
- Do not shake COSENTYX.
- Throw away any expired or unused COSENTYX.

Keep COSENTYX and all medicines out of the reach of children.

General information about the safe and effective use of COSENTYX.
Medicines are sometimes prescribed for purposes other than those listed in a Medication Guide. Do not use COSENTYX for a condition for which it was not prescribed. Do not give COSENTYX to other people, even if they have the same symptoms that you have. It may harm them. You can ask your pharmacist or healthcare provider for information about COSENTYX that is written for health professionals.

What are the ingredients in COSENTYX?
Active ingredient: secukinumab.
Inactive ingredients:
L-histidine/histidine hydrochloride monohydrate, L-methionine, polysorbate 80, trehalose dihydrate, and sterile water for injection.
Manufactured by: Novartis Pharmaceuticals Corporation, East Hanover, New Jersey 07936, U.S. License Number 1244
For more information, call 1-888-669-6682 or go to www.COSENTYX.com

This Medication Guide has been approved by the U.S. Food and Drug Administration.

Revised: August 2024

T2024-65

INSTRUCTIONS FOR USE

COSENTYX® [koe-sen-tix]

(secukinumab)

injection, for subcutaneous use

300 mg/2 mL single-dose prefilled syringe

Be sure that you read, understand, and follow this Instructions for Use before injecting COSENTYX. Your healthcare provider should show you how to prepare and inject COSENTYX properly using the prefilled syringe before you use it for the first time. Talk to your healthcare provider if you have any questions.

Important Information You Need to Know Before Injecting COSENTYX:

- Do not use the COSENTYX prefilled syringe if either the seal on the outside carton or the seal of the blister are broken. Keep the COSENTYX prefilled syringe in the sealed carton until you are ready to use it.
- Do not use the COSENTYX prefilled syringe if the syringe has been dropped onto a hard surface or dropped after removing the needle cap.
- Do not shake the COSENTYX prefilled syringe.
- The prefilled syringe has a needle guard that will be activated to cover the needle after the injection is finished. The needle guard will help to prevent needle stick injuries to anyone who handles the prefilled syringe.
- Do not remove the needle cap until just before you give the injection.
- Avoid touching the syringe guard wings before use. Touching them may cause the syringe guard to be activated too early.
- Throw away (dispose of) the used COSENTYX prefilled syringe right away after use. Do not re-use the COSENTYX prefilled syringe. See “How should I dispose of the used COSENTYX prefilled syringe?” at the end of this Instructions for Use.

How should I store COSENTYX?

- Store your carton of COSENTYX prefilled syringe in a refrigerator, between 36°F to 46°F (2°C to 8°C).
- Keep the COSENTYX prefilled syringe in the original carton until ready to use to protect from light.
- Do not freeze the COSENTYX prefilled syringe.
- Throw away (dispose of) any expired or unused COSENTYX prefilled syringes.

Keep COSENTYX and all medicines out of the reach of children.
COSENTYX prefilled syringe parts (see Figure A):

Figure A

What you need for your injection:

Included in the carton:

A new COSENTYX prefilled syringe.

Each COSENTYX prefilled syringe contains 300 mg of COSENTYX. Check to make sure that you have the correct medicine and dose.

Not included in the carton (see Figure B):
• 1 Alcohol wipe
• 1 Cotton ball or gauze
• Sharps disposal container
See “How should I dispose of the used COSENTYX prefilled syringe?” at the end of this Instructions for Use.

Figure B

Prepare the COSENTYX 300 mg prefilled syringe

Step 1. Find a clean, well-lit, flat work surface.

Step 2. Take the carton containing the COSENTYX prefilled syringe out of the refrigerator and leave it unopened on your work surface for about 30 to 45 minutes so that it reaches room temperature.

Step 3. Wash your hands well with soap and water.

Step 4. Remove the COSENTYX prefilled syringe from the outer carton and take it out of the blister.

Step 5. Look through the viewing window on the COSENTYX prefilled syringe. The liquid inside should be clear. The color may be colorless to slightly yellow. You may see a small air bubble in the liquid. This is normal. Do not use the prefilled syringe if the liquid contains visible particles, or if the liquid is cloudy or discolored.

Step 6. Do not use the COSENTYX prefilled syringe if it is broken. Return the prefilled syringe and the package it came in to the pharmacy.

Step 7. Do not use the COSENTYX prefilled syringe if the expiration date has passed.

Choose and clean the injection site

- Areas of your body that you may use as injection sites include:
  - the front of your thighs (see Figure C)
  - the lower stomach-area (abdomen), but not the area 2 inches around your navel (belly button) (see Figure C)
  - the upper outer arms, if a caregiver or healthcare provider is giving you the injection (see Figure D)
- Choose a different site for each injection of COSENTYX.
- Do not inject into areas where the skin is tender, bruised, red, scaly, or hard, or in an area of skin that is affected by psoriasis. Avoid areas with scars or stretch marks.

Figure C

Step 8. Using a circular motion, clean the injection site with the alcohol wipe. Leave it to dry before injecting. Do not touch the cleaned area again before injecting.

Figure D

Giving the injection

Step 9. Carefully remove the needle cap from the COSENTYX prefilled syringe (see Figure E). Throw away the needle cap. You may see a drop of liquid at the end of the needle. This is normal.

Figure E

Step 10. With one hand gently pinch the skin at the injection site. With your other hand insert the needle into your skin at a 45-degree angle as shown (see Figure F). Push the needle all the way in to make sure that you inject your full dose.

Figure F

Step 11. Hold the COSENTYX prefilled syringe finger grips as shown (see Figure G). Slowly press down on the plunger as far as it will go, so that the plunger head is completely between the syringe guard wings. This will make sure that the syringe guard has been activated.
Step 12. Continue to press fully on the plunger for an additional 5 seconds. Hold the syringe in place for the full 5 seconds.

Figure G

Step 13. Keep the plunger fully depressed while you carefully pull the needle straight out from the injection site (see Figure H).

Figure H

Step 14. Slowly release the plunger and allow the syringe guard to automatically cover the exposed needle (see Figure I).
Step 15. There may be a small amount of blood at the injection site. You can press a cotton ball or gauze over the injection site and hold it for 10 seconds. Do not rub the injection site. You may cover the injection site with a small adhesive bandage, if needed.

Figure I

How should I dispose of the used COSENTYX prefilled syringe?

Step 16. Put your used prefilled syringe in an FDA-cleared sharps disposal container right away after use (see Figure J). Do not throw away (dispose of) the prefilled syringe in your household trash.
If you do not have an FDA-cleared sharps disposal container, you may use a household container that is:

- made of a heavy-duty plastic,
- can be closed with a tight-fitting, puncture-resistant lid, without sharps being able to come out,
- upright and stable during use,
- leak-resistant, and
- properly labeled to warn of hazardous waste inside the container.

When your sharps disposal container is almost full, you will need to follow your community guidelines for the right way to dispose of your sharps disposal container. There may be state or local laws about how you should throw away used needles, syringes, and prefilled syringes. For more information about safe sharps disposal, and for specific information about sharps disposal in the state that you live in, go to the FDA’s website at: http://www.fda.gov/safesharpsdisposal.

Figure J

Manufactured by:
Novartis Pharmaceuticals Corporation
East Hanover, New Jersey 07936
US License Number 1244

© Novartis

This Instructions for Use has been approved by the U.S. Food and Drug Administration.

Issued: July 2023

T2023-42

INSTRUCTIONS FOR USE

COSENTYX® [koe-sen-tix]

(secukinumab)

injection, for subcutaneous use

150 mg/mL single-dose prefilled syringe

Be sure that you read, understand, and follow this Instructions for Use before injecting COSENTYX. Your healthcare provider should show you how to prepare and inject COSENTYX properly using the prefilled syringe before you use it for the first time. Children should not inject COSENTYX themselves using the prefilled syringe. An adult caregiver should prepare and inject COSENTYX after receiving proper training in subcutaneous injection technique. Talk to your healthcare provider if you have any questions.

Important Information You Need to Know Before Injecting COSENTYX:

- Do not use the COSENTYX prefilled syringe if either the seal on the outside carton or the seal of the blister are broken. Keep the COSENTYX prefilled syringe in the sealed carton until you are ready to use it.
- Do not use the COSENTYX prefilled syringe if the syringe has been dropped onto a hard surface or dropped after removing the needle cap.
- Do not shake the COSENTYX prefilled syringe.
- The needle caps of the prefilled syringes contain latex. Do not handle the prefilled syringes if you are sensitive to latex.
- The prefilled syringe has a needle guard that will be activated to cover the needle after the injection is finished. The needle guard will help to prevent needle stick injuries to anyone who handles the prefilled syringe.
- Do not remove the needle cap until just before you give the injection.
- Avoid touching the syringe guard wings before use. Touching them may cause the syringe guard to be activated too early.
- Throw away (dispose of) the used COSENTYX prefilled syringe right away after use. Do not re-use the COSENTYX prefilled syringe. See “How should I dispose of used COSENTYX prefilled syringes?” at the end of this Instructions for Use.

How should I store COSENTYX?

- Store your carton of COSENTYX prefilled syringes in a refrigerator, between 36°F to 46°F (2°C to 8°C).
- Keep the COSENTYX prefilled syringes in the original carton until ready to use to protect from light.
- The COSENTYX prefilled syringes may be stored at room temperature, up to 86°F (30°C), for up to 4 days.
- Write the date the COSENTYX prefilled syringes were removed from and returned to the refrigerator in the space provided on the carton.
- Throw away the COSENTYX prefilled syringe if it has been kept outside of the refrigerator over 4 days.
- COSENTYX prefilled syringe may be returned to the refrigerator only 1 time and must be stored between 36°F to 46°F (2°C to 8°C) until you use it or until it expires.
- Do not freeze the COSENTYX prefilled syringes.
- Throw away (dispose of) any expired or unused COSENTYX prefilled syringes.

Keep COSENTYX and all medicines out of the reach of children.

COSENTYX prefilled syringe parts (see Figure A):

Figure A

What you need for your injection:

Included in the carton:

A new COSENTYX prefilled syringe.

Each COSENTYX prefilled syringe contains 150 mg of COSENTYX. Check to make sure that you have the correct medicine and dose.

- If your prescribed dose of COSENTYX is 150 mg, you must give 1 injection.
- If your prescribed dose of COSENTYX is 300 mg, you must give 2 injections.

Not included in the carton (see Figure B):
• 1 Alcohol wipe
• 1 Cotton ball or gauze
• Sharps disposal container
See “How should I dispose of used COSENTYX prefilled syringes?” at the end of this Instructions for Use.

Figure B

Prepare the COSENTYX 150 mg prefilled syringe

Step 1. Find a clean, well-lit, flat work surface.

Step 2. Take the carton containing the COSENTYX prefilled syringe out of the refrigerator and leave it unopened on your work surface for about 15 to 30 minutes so that it reaches room temperature.

Step 3. Wash your hands well with soap and water.

Step 4. Remove the COSENTYX prefilled syringe from the outer carton and take it out of the blister.

Step 5. Look through the viewing window on the COSENTYX prefilled syringe. The liquid inside should be clear. The color may be colorless to slightly yellow. You may see a small air bubble in the liquid. This is normal. Do not use the prefilled syringe if the liquid contains visible particles, or if the liquid is cloudy or discolored.

Step 6. Do not use the COSENTYX prefilled syringe if it is broken. Return the prefilled syringe and the package it came in to the pharmacy.

Step 7. Do not use the COSENTYX prefilled syringe if the expiration date has passed.

Choose and clean the injection site

- Areas of your body that you may use as injection sites include:
  - the front of your thighs (see Figure C)
  - the lower stomach-area (abdomen), but not the area 2 inches around your navel (belly button) (see Figure C)
  - the upper outer arms, if a caregiver or healthcare provider is giving you the injection (see Figure D)
- Choose a different site for each injection of COSENTYX.
- Do not inject into areas where the skin is tender, bruised, red, scaly, or hard, or in an area of skin that is affected by psoriasis. Avoid areas with scars or stretch marks.

Figure C

Step 8. Using a circular motion, clean the injection site with the alcohol wipe. Leave it to dry before injecting. Do not touch the cleaned area again before injecting.

Figure D

Giving the injection

Step 9. Carefully remove the needle cap from the COSENTYX prefilled syringe (see Figure E). Throw away the needle cap. You may see a drop of liquid at the end of the needle. This is normal.

Figure E

Step 10. With one hand gently pinch the skin at the injection site. With your other hand insert the needle into your skin at a 45-degree angle as shown (see Figure F). Push the needle all the way in to make sure that you inject your full dose.

Figure F

Step 11. Hold the COSENTYX prefilled syringe finger grips as shown (see Figure G). Slowly press down on the plunger as far as it will go, so that the plunger head is completely between the syringe guard wings. This will make sure that the syringe guard has been activated.
Step 12. Continue to press fully on the plunger for an additional 5 seconds. Hold the syringe in place for the full 5 seconds.

Figure G

Step 13. Keep the plunger fully depressed while you carefully pull the needle straight out from the injection site (see Figure H).

Figure H

Step 14. Slowly release the plunger and allow the syringe guard to automatically cover the exposed needle (see Figure I).
Step 15. There may be a small amount of blood at the injection site. You can press a cotton ball or gauze over the injection site and hold it for 10 seconds. Do not rub the injection site. You may cover the injection site with a small adhesive bandage, if needed.

Figure I

If your prescribed dose of COSENTYX is 300 mg, repeat Steps 4 through 15 with a new COSENTYX prefilled syringe.
How should I dispose of used COSENTYX prefilled syringes?

Step 16. Put your used prefilled syringes in an FDA-cleared sharps disposal container right away after use (see Figure J). Do not throw away (dispose of) the prefilled syringes in your household trash.
If you do not have an FDA-cleared sharps disposal container, you may use a household container that is:

- made of a heavy-duty plastic,
- can be closed with a tight-fitting, puncture-resistant lid, without sharps being able to come out,
- upright and stable during use,
- leak-resistant, and
- properly labeled to warn of hazardous waste inside the container.

When your sharps disposal container is almost full, you will need to follow your community guidelines for the right way to dispose of your sharps disposal container. There may be state or local laws about how you should throw away used needles, syringes, and prefilled syringes. For more information about safe sharps disposal, and for specific information about sharps disposal in the state that you live in, go to the FDA’s website at: http://www.fda.gov/safesharpsdisposal.

Figure J

Manufactured by:
Novartis Pharmaceuticals Corporation
East Hanover, New Jersey 07936
US License Number 1244

© Novartis

This Instructions for Use has been approved by the U.S. Food and Drug Administration.

Revised: July 2023

T2023-43

INSTRUCTIONS FOR USE

COSENTYX® [koe-sen-tix]

(secukinumab)

injection, for subcutaneous use

75 mg/0.5 mL single-dose prefilled syringe

Be sure that you read, understand, and follow this Instructions for Use before injecting COSENTYX. Your healthcare provider should show you how to prepare and inject COSENTYX properly using the prefilled syringe before you use it for the first time. Children should not inject COSENTYX themselves using the prefilled syringe. An adult caregiver should prepare and inject COSENTYX after receiving proper training in subcutaneous injection technique. Talk to your healthcare provider if you have any questions.

Important Information You Need to Know Before Injecting COSENTYX:

- Do not use the COSENTYX prefilled syringe if either the seal on the outside carton or the seal of the blister are broken. Keep the COSENTYX prefilled syringe in the sealed carton until you are ready to use it.
- Do not use the COSENTYX prefilled syringe if the syringe has been dropped onto a hard surface or dropped after removing the needle cap.
- Do not shake the COSENTYX prefilled syringe.
- The needle cap of the prefilled syringe contains latex. Do not handle the prefilled syringe if you are sensitive to latex.
- The prefilled syringe has a needle guard that will be activated to cover the needle after the injection is finished. The needle guard will help to prevent needle stick injuries to anyone who handles the prefilled syringe.
- Do not remove the needle cap until just before you give the injection.
- Avoid touching the syringe guard wings before use. Touching them may cause the syringe guard to be activated too early.
- Throw away (dispose of) the used COSENTYX prefilled syringe right away after use. Do not re-use the COSENTYX prefilled syringe. See “How should I dispose of the used COSENTYX prefilled syringe?” at the end of this Instructions for Use.

How should I store COSENTYX?

- Store your carton of COSENTYX prefilled syringe in a refrigerator, between 36°F to 46°F (2°C to 8°C).
- Keep the COSENTYX prefilled syringe in the original carton until ready to use to protect from light.
- COSENTYX prefilled syringe may be stored at room temperature, up to 86°F (30°C), for up to 4 days.
- Write the date COSENTYX prefilled syringe was removed from and returned to the refrigerator in the space provided on the carton.
- Throw away COSENTYX prefilled syringe if it has been kept outside of the refrigerator over 4 days.
- COSENTYX prefilled syringe may be returned to the refrigerator only 1 time and must be stored between 36°F to 46°F (2°C to 8°C) until you use it or until it expires.
- Do not freeze the COSENTYX prefilled syringe.
- Throw away (dispose of) any expired or unused COSENTYX prefilled syringe.

Keep COSENTYX and all medicines out of the reach of children.

COSENTYX prefilled syringe parts (see Figure A):

Figure A

What you need for your injection:

Included in the carton:

A new COSENTYX prefilled syringe.

Each COSENTYX prefilled syringe contains 75 mg of COSENTYX. Check to make sure that you have the correct medicine and dose.

Not included in the carton (see Figure B):
• 1 Alcohol wipe
• 1 Cotton ball or gauze
• Sharps disposal container
See “How should I dispose of the used COSENTYX prefilled syringe?” at the end of this Instructions for Use.

Figure B

Prepare the COSENTYX 75 mg prefilled syringe

Step 1. Find a clean, well-lit, flat work surface.

Step 2. Take the carton containing the COSENTYX prefilled syringe out of the refrigerator and leave it unopened on your work surface for about 15 to 30 minutes so that it reaches room temperature.

Step 3. Wash your hands well with soap and water.

Step 4. Remove the COSENTYX prefilled syringe from the outer carton and take it out of the blister.

Step 5. Look through the viewing window on the COSENTYX prefilled syringe. The liquid inside should be clear. The color may be colorless to slightly yellow. You may see a small air bubble in the liquid. This is normal. Do not use the prefilled syringe if the liquid contains visible particles, or if the liquid is cloudy or discolored.

Step 6. Do not use the COSENTYX prefilled syringe if it is broken. Return the prefilled syringe and the package it came in to the pharmacy.

Step 7. Do not use the COSENTYX prefilled syringe if the expiration date has passed.

Choose and clean the injection site

- Areas of your body that you may use as injection sites include:
  - the front of your thighs (see Figure C)
  - the lower stomach-area (abdomen), but not the area 2 inches around your navel (belly button) (see Figure C)
  - the upper outer arms (see Figure D)
- Choose a different site for each injection of COSENTYX.
- Do not inject into areas where the skin is tender, bruised, red, scaly, or hard, or in an area of skin that is affected by psoriasis. Avoid areas with scars or stretch marks.

Figure C

Step 8. Using a circular motion, clean the injection site with the alcohol wipe. Leave it to dry before injecting. Do not touch the cleaned area again before injecting.

Figure D

Giving the injection

Step 9. Carefully remove the needle cap from the COSENTYX prefilled syringe (see Figure E). Throw away the needle cap. You may see a drop of liquid at the end of the needle. This is normal.

Figure E

Step 10. With one hand gently pinch the skin at the injection site. With your other hand insert the needle into your skin at a 45-degree angle as shown (see Figure F). Push the needle all the way in to make sure that you inject your full dose.

Figure F

Step 11. Hold the COSENTYX prefilled syringe finger grips as shown (see Figure G). Slowly press down on the plunger as far as it will go, so that the plunger head is completely between the syringe guard wings. This will make sure that the syringe guard has been activated.
Step 12. Continue to press fully on the plunger for an additional 5 seconds. Hold the syringe in place for the full 5 seconds.

Figure G

Step 13. Keep the plunger fully depressed while you carefully pull the needle straight out from the injection site (see Figure H).

Figure H

Step 14. Slowly release the plunger and allow the syringe guard to automatically cover the exposed needle (see Figure I).
Step 15. There may be a small amount of blood at the injection site. You can press a cotton ball or gauze over the injection site and hold it for 10 seconds. Do not rub the injection site. You may cover the injection site with a small adhesive bandage, if needed.

Figure I

How should I dispose of the used COSENTYX prefilled syringe?
Step 16. Put your used prefilled syringe in an FDA-cleared sharps disposal container right away after use (see Figure J). Do not throw away (dispose of) the prefilled syringe in your household trash.
If you do not have an FDA-cleared sharps disposal container, you may use a household container that is:

- made of a heavy-duty plastic,
- can be closed with a tight-fitting, puncture-resistant lid, without sharps being able to come out,
- upright and stable during use,
- leak-resistant, and
- properly labeled to warn of hazardous waste inside the container.

When your sharps disposal container is almost full, you will need to follow your community guidelines for the right way to dispose of your sharps disposal container. There may be state or local laws about how you should throw away used needles, syringes, and prefilled syringes. For more information about safe sharps disposal, and for specific information about sharps disposal in the state that you live in, go to the FDA’s website at: http://www.fda.gov/safesharpsdisposal.

Figure J

Manufactured by:
Novartis Pharmaceuticals Corporation
East Hanover, New Jersey 07936
US License Number 1244

© Novartis

This Instructions for Use has been approved by the U.S. Food and Drug Administration.

Revised: July 2023

T2023-44

INSTRUCTIONS FOR USE
COSENTYX® [koe-sen-tix]
(secukinumab)
injection, for subcutaneous use
300 mg/2 mL single-dose UnoReady® pen

Be sure that you read, understand, and follow this Instructions for Use before injecting COSENTYX. Your healthcare provider should show you how to prepare and properly inject with the COSENTYX UnoReady pen before you use it for the first time. Talk to your healthcare provider if you have any questions.

Cosentyx UnoReady pen parts

Figure A

The COSENTYX UnoReady pen is shown in Figure A with the cap removed.
Do not remove the cap until you are ready to inject.

Important information You Need to Know Before Injecting COSENTYX:

- Do not use the COSENTYX UnoReady pen if the seal on the outer carton is broken. Keep the COSENTYX UnoReady pen in the sealed outer carton until you are ready to use it.
- Do not shake the COSENTYX UnoReady pen.
- If you drop your COSENTYX UnoReady pen, do not use it if it looks damaged, or if you dropped it with the cap removed.
- The needle is covered by the needle guard and the needle will not be seen. Do not touch or push the needle guard because you could get a needle stick.
- Throw away (dispose of) the used COSENTYX UnoReady pen right away after use.
- Do not re-use the COSENTYX UnoReady pen. See “Step 9. Disposing of the used COSENTYX UnoReady pen” at the end of this Instructions for Use.

Storing the COSENTYX UnoReady pen

- Store your carton of COSENTYX UnoReady pen in a refrigerator between 36°F and 46°F (2°C and 8°C).
- Keep the COSENTYX UnoReady pen in the original carton until ready to use to protect from light.
- Do not freeze the COSENTYX UnoReady pen.
- Throw away (dispose of) any expired or unused COSENTYX UnoReady pen.

Keep the COSENTYX UnoReady pen and all medicines out of the reach of children.

What you need for your injection

Figure B

Included in the carton (see Figure B)

- A new COSENTYX UnoReady pen
  Each COSENTYX UnoReady pen contains 300 mg of COSENTYX. Check to make sure that you have the correct medicine and dose.

Figure C

Not included in the carton (see Figure C)

- 1 Alcohol wipe
- 1 Cotton ball or gauze
- Sharps disposal container. See “Step 9. Disposing of the used COSENTYX UnoReady pen” at the end of this Instructions for Use.

Prepare to inject

Figure D

Step 1. Bring to room temperature
Take the carton containing the COSENTYX UnoReady pen out of the refrigerator (see Figure D) and leave it unopened for 30 to 45 minutes before injecting to allow it to reach room temperature.

Figure E

Step 2. Important safety checks before you inject (see Figure E)

- Look at the expiration date (EXP) on your COSENTYX UnoReady pen. Do not use the COSENTYX UnoReady pen if the expiration date has passed.
- Look through the viewing window. The liquid should be clear. Its color may vary from colorless to slightly yellow.
- Do not use if the liquid contains visible particles, is cloudy or is discolored. You may see air bubbles, which is normal.

Contact your healthcare provider or pharmacist if the COSENTYX UnoReady pen fails any of these checks.

Figure F

Step 3. Choose the injection site

- The recommended site is the front of the thighs. You may also use the lower abdomen, but not the area 2 inches around the navel (belly button) (see Figure F).
- Choose a different site each time you give an injection.
- Do not inject into areas where the skin is tender, bruised, red, scaly, or hard or in an area of skin that is affected by psoriasis. Avoid areas with scars or stretch marks.

Figure G

- If a caregiver or healthcare provider is giving you your injection, they may also inject into your outer upper arm (see Figure G).

Figure H

Step 4. Clean the injection site

- Wash your hands well with soap and water.
- Using a circular motion, clean the injection site with the alcohol wipe (see Figure H). Leave it to dry before injecting.
- Do not touch the cleaned area again before injecting.

Injecting with the COSENTYX UnoReady pen

Figure I

Step 5. Remove the cap

- Only remove the cap when you are ready to use the COSENTYX UnoReady pen.
- Pull the cap straight off (see Figure I). Do not twist the cap.
- Throw away the cap. Do not try to re-attach the cap.
- Use the COSENTYX UnoReady pen within 5 minutes of removing the cap.

Figure J

Step 6. Position the COSENTYX UnoReady pen
Hold the COSENTYX UnoReady pen at 90 degrees against the cleaned injection site with the viewing window facing you (see Figure J).

Step 7. Injecting with the COSENTYX UnoReady pen as described below (see Figure K)

Figure K

After the injection

Figure L

Step 8. Check that the green indicator has filled the window (see Figure L)

- This means the medicine has been delivered. Contact your healthcare provider or pharmacist if the green indicator is not visible or does not fill the window.
- There may be a small amount of blood at the injection site. You can press a cotton ball or gauze over the injection site and hold it for a few seconds. Do not rub the injection site. You may cover the injection site with a small adhesive bandage, if needed.

Figure M

Step 9. Disposing of the used COSENTYX UnoReady pen

- Put your used COSENTYX UnoReady pen in an FDA-cleared sharps disposal container right away after use (see Figure M). Do not throw away (dispose of) the COSENTYX UnoReady pen in your household trash. If you do not have an FDA-cleared sharps disposal container, you may use a household container that is:
  - made of a heavy-duty plastic,
  - can be closed with a tight-fitting, puncture-resistant lid, without sharps being able to come out,
  - upright and stable during use,
  - leak-resistant, and
  - properly labeled to warn of hazardous waste inside the container.
- When your sharps disposal container is almost full, you will need to follow your community guidelines for the right way to dispose of your sharps disposal container. There may be state or local laws about how you should throw away used needles, syringes, and COSENTYX UnoReady pens.

For more information about safe sharps disposal, and for specific information about sharps disposal in the state that you live in, go to the FDA’s website at: http://www.fda.gov/safesharpsdisposal.

Manufactured by:
Novartis Pharmaceuticals Corporation
East Hanover, New Jersey 07936
US License Number 1244

© Novartis

This Instructions for Use has been approved by the U.S. Food and Drug Administration.

Issued: July 2023

T2023-45

INSTRUCTIONS FOR USE

COSENTYX® [koe-sen-tix]

(secukinumab)

injection, for subcutaneous use

150 mg/mL single-dose Sensoready® pen

Be sure that you read, understand, and follow this Instructions for Use before injecting COSENTYX. Your healthcare provider should show you how to prepare and inject COSENTYX properly using the Sensoready pen before you use it for the first time. Children should not inject COSENTYX themselves using the Sensoready pen. An adult caregiver should prepare and inject COSENTYX after receiving proper training in subcutaneous injection technique. Talk to your healthcare provider if you have any questions.

Important Information You Need to Know Before Injecting COSENTYX:

- Do not use the COSENTYX Sensoready pen if either the seal on the outer carton or the seal on the pen is broken. Keep the COSENTYX Sensoready pen in the sealed outer carton until you are ready to use it.
- Do not shake the COSENTYX Sensoready pen.
- The caps of the Sensoready pens contain latex. Do not handle the Sensoready pens if you are sensitive to latex.
- If you drop your COSENTYX Sensoready pen, do not use it if the Sensoready pen looks damaged, or if you dropped it with the cap removed.
- Throw away (dispose of) the used COSENTYX Sensoready pen right away after use. Do not re-use the COSENTYX Sensoready pen. See “How should I dispose of used COSENTYX Sensoready pens?” at the end of this Instructions for Use.

How should I store COSENTYX?

- Store your carton of COSENTYX Sensoready pens in a refrigerator, between 36°F to 46°F (2°C to 8°C).
- Keep the COSENTYX Sensoready pens in the original carton until ready to use to protect from light.
- The COSENTYX Sensoready pens may be stored at room temperature, up to 86°F (30°C), for up to 4 days.
- Write the date the COSENTYX Sensoready pens were removed from and returned to the refrigerator in the space provided on the carton.
- Throw away the COSENTYX Sensoready pen if it has been kept outside of the refrigerator over 4 days.
- COSENTYX Sensoready pen may be returned to the refrigerator only 1 time and must be stored between 36°F to 46°F (2°C to 8°C) until you use it or until it expires.
- Do not freeze the COSENTYX Sensoready pens.
- Throw away (dispose of) any expired or unused COSENTYX Sensoready pens.

Keep COSENTYX and all medicines out of the reach of children.

COSENTYX Sensoready pen parts (see Figure A):

Figure A

The COSENTYX Sensoready pen is shown above with the cap removed. Do not remove the cap until you are ready to inject.

What you need for your injection:

Included in the carton:
A new COSENTYX Sensoready pen (see Figure B).
Each COSENTYX Sensoready pen contains 150 mg of COSENTYX. Check to make sure that you have the correct medicine and dose.

- If your prescribed dose of COSENTYX is 150 mg, you must give 1 injection.
- If your prescribed dose of COSENTYX is 300 mg, you must give 2 injections.

Figure B

Not included in the carton (see Figure C):

- 1 Alcohol wipe
- 1 Cotton ball or gauze
- Sharps disposal container.

See “How should I dispose of used COSENTYX Sensoready pens?” at the end of this Instructions for Use.

Figure C

Before your injection:
Take the carton containing the COSENTYX Sensoready pen out of the refrigerator and leave it unopened for about 15 to 30 minutes before injecting to allow it to reach room temperature.

Step 1. Important safety checks before you inject (see Figure D):

- Look through the viewing window. The liquid should be clear. Its color may vary from colorless to slightly yellow.
  Do not use if the liquid contains visible particles, is cloudy or is discolored. You may see a small air bubble, which is normal.
- Look at the expiration date (EXP) on your Sensoready pen. Do not use your COSENTYX Sensoready pen if the expiration date has passed.

Contact your pharmacist if the COSENTYX Sensoready pen fails any of these checks.

Figure D

Step 2. Choose the injection site:

- The recommended site is the front of the thighs. You may also use the lower abdomen, but not the area 2 inches around the navel (belly button) (see Figure E).
- Choose a different site each time you give an injection.
- Do not inject into areas where the skin is tender, bruised, red, scaly, or hard, or in an area of skin that is affected by psoriasis. Avoid areas with scars or stretch marks.

Figure E

- If a caregiver or healthcare provider is giving you your injection, they may also inject into your outer upper arm (see Figure F).

Figure F

Step 3. Cleaning the injection site:

- Wash your hands well with soap and water.
- Using a circular motion, clean the injection site with the alcohol wipe. Leave it to dry before injecting (see Figure G).
- Do not touch the cleaned area again before injecting.

Figure G

Your injection:

Step 4. Removing the cap:

- Only remove the cap when you are ready to use the COSENTYX Sensoready pen.
- Twist off the cap in the direction of the arrow (see Figure H).
- Throw away the cap. Do not try to re-attach the cap.
- Use the COSENTYX Sensoready pen within 5 minutes of removing the cap.

Figure H

Step 5. Holding the COSENTYX Sensoready pen:

- Hold the COSENTYX Sensoready pen at 90 degrees to the cleaned injection site (see Figure I).

Figure I

Important: During the injection you will hear 2 loud clicks:

- The 1st click indicates that the injection has started.
- Several seconds later a 2nd click will indicate that the injection is almost finished.

You must keep holding the COSENTYX Sensoready pen firmly against the skin until you see a green indicator fill the window and stop moving.

Step 6. Starting the injection:

- Press the COSENTYX Sensoready pen firmly against the skin to start the injection (see Figure J).
- The 1st click indicates the injection has started.
- Keep holding the COSENTYX Sensoready pen firmly against the skin.
- The green indicator shows the progress of the injection.

Figure J

Step 7. Completing the injection:

- Listen for the 2nd click. This indicates the injection is almost complete.
- Check the green indicator fills the window and has stopped moving (see Figure K).
- The COSENTYX Sensoready pen can now be removed.

Figure K

After the injection:

Step 8. Check the green indicator fills the window (see Figure L):

- This means the medicine has been delivered. Contact your healthcare provider if the green indicator is not visible.
- There may be a small amount of blood at the injection site. You can press a cotton ball or gauze over the injection site and hold it for 10 seconds. Do not rub the injection site. You may cover the injection site with a small adhesive bandage, if needed.

If your prescribed dose of COSENTYX is 300 mg, repeat Steps 1 through 8 with a new COSENTYX Sensoready pen.

Figure L

How should I dispose of used COSENTYX Sensoready pens?

Step 9. Put your used Sensoready pen in an FDA-cleared sharps disposal container right away after use (see Figure M). Do not throw away (dispose of) the Sensoready pens in your household trash.
If you do not have an FDA-cleared sharps disposal container, you may use a household container that is:

- made of a heavy-duty plastic,
- can be closed with a tight-fitting, puncture-resistant lid, without sharps being able to come out,
- upright and stable during use,
- leak-resistant, and
- properly labeled to warn of hazardous waste inside the container.

When your sharps disposal container is almost full, you will need to follow your community guidelines for the right way to dispose of your sharps disposal container. There may be state or local laws about how you should throw away used needles, syringes, and Sensoready pens. For more information about safe sharps disposal, and for specific information about sharps disposal in the state that you live in, go to the FDA’s website at: http://www.fda.gov/safesharpsdisposal.

Figure M

Manufactured by:
Novartis Pharmaceuticals Corporation
East Hanover, New Jersey 07936
US License Number 1244

© Novartis

This Instructions for Use has been approved by the U.S. Food and Drug Administration.

Revised: July 2023

T2023-46

PRINCIPAL DISPLAY PANEL

NDC 0078-0639-97

Rx only

Cosentyx®

(secukinumab)

Injection

Single-dose Prefilled Syringe

150 mg/mL

1 Prefilled Syringe

ATTENTION: Dispense with enclosed Medication Guide.

For Subcutaneous Use Only

Sterile Solution - Contains No Preservative

Caution: Contains Natural Rubber Latex Which May Cause Allergic Reaction.

NOVARTIS

PRINCIPAL DISPLAY PANEL

NDC 0078-1056-97

Rx only

Cosentyx®

(secukinumab)
Injection

75 mg/0.5 mL

1 Single-dose Prefilled Syringe

For Subcutaneous Use Only

Caution: Contains Natural Rubber Latex
Which May Cause Allergic Reaction.

ATTENTION:
Dispense with enclosed Medication Guide.

NOVARTIS

PRINCIPAL DISPLAY PANEL

NDC 0078-1070-68

Rx only

Cosentyx®

(secukinumab)
Injection

Single-dose prefilled UnoReady® Pen

300 mg/2 mL

For Subcutaneous Use Only

1 UnoReady® Pen

ATTENTION: Dispense with enclosed Medication Guide.

Carton contains: • 1 Single-dose prefilled UnoReady® Pen • Prescribing Information • Medication Guide • Instructions for Use

NOVARTIS

PRINCIPAL DISPLAY PANEL

NDC 0078-1168-61

Rx only

Cosentyx®

(secukinumab)
Injection

125 mg/5 mL
(25 mg/mL)

For Intravenous Infusion After Dilution.

ATTENTION: Dispense with enclosed Medication Guide.

1 Single-Dose Vial.

Discard Unused Portion.

NOVARTIS